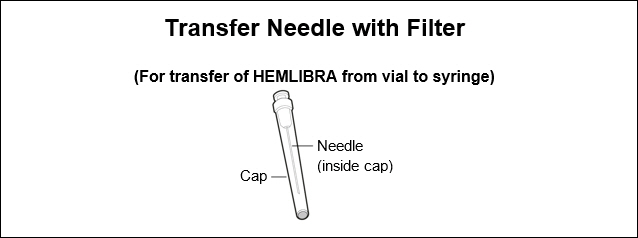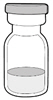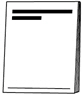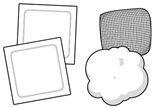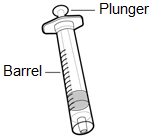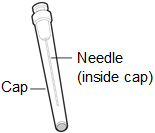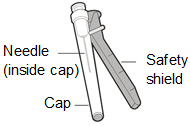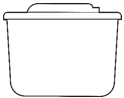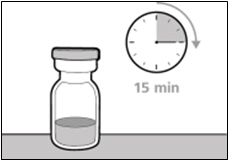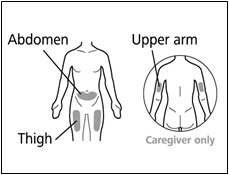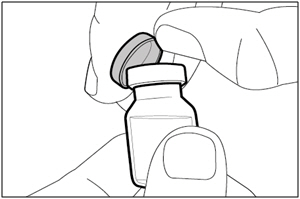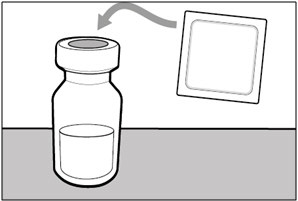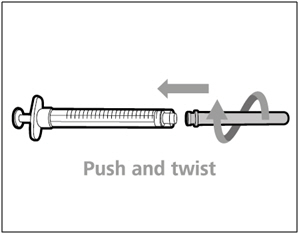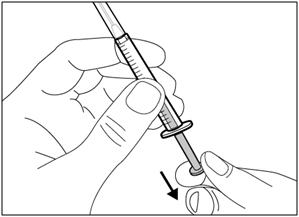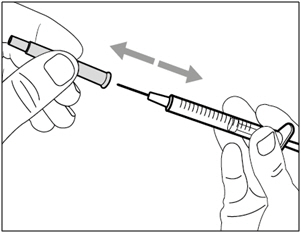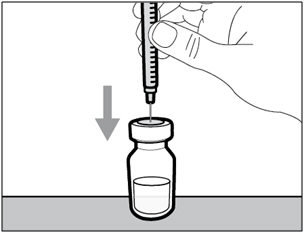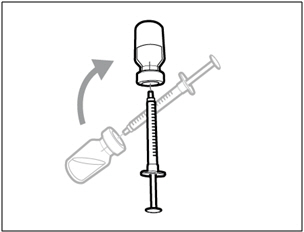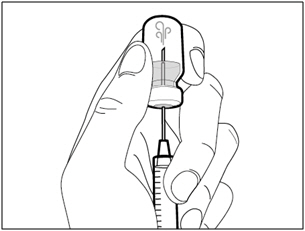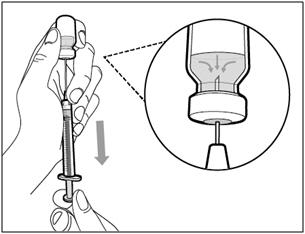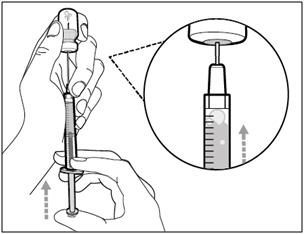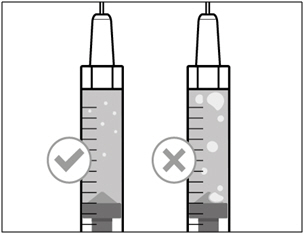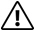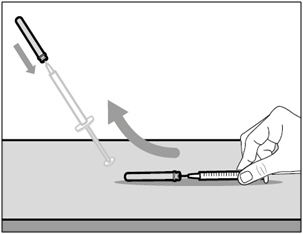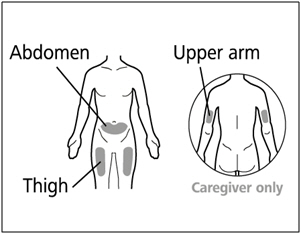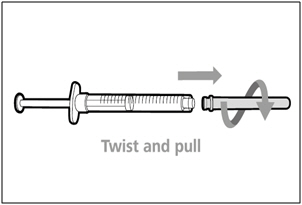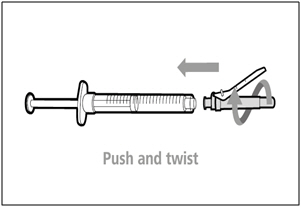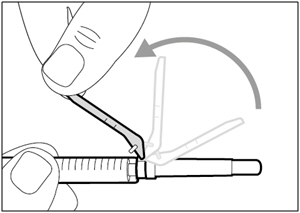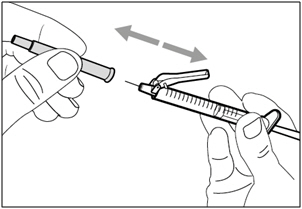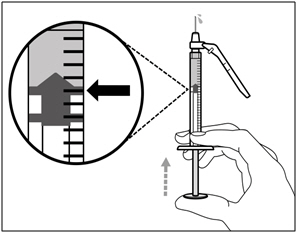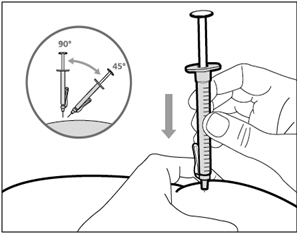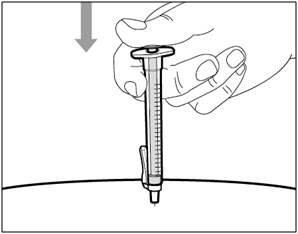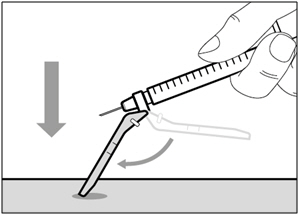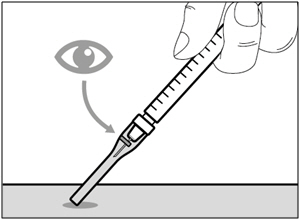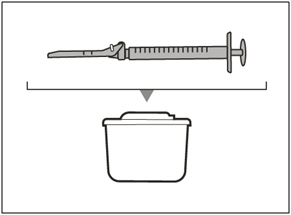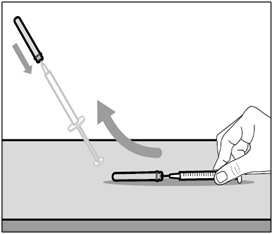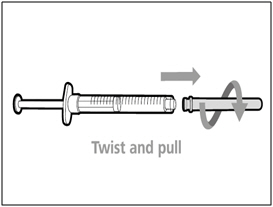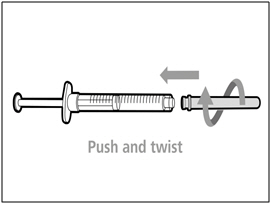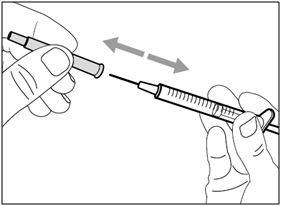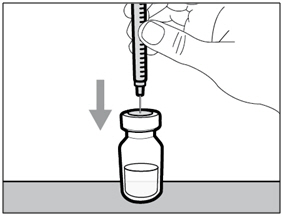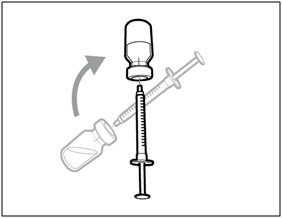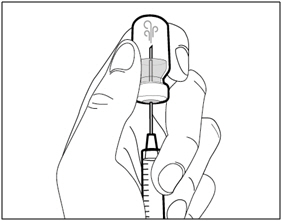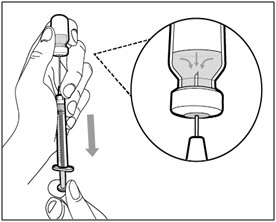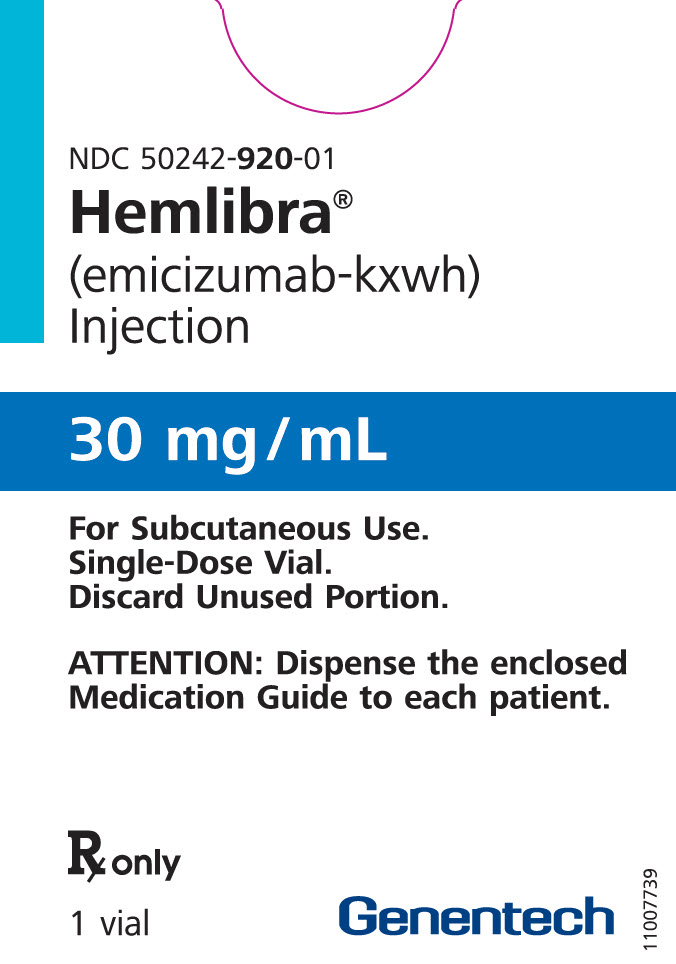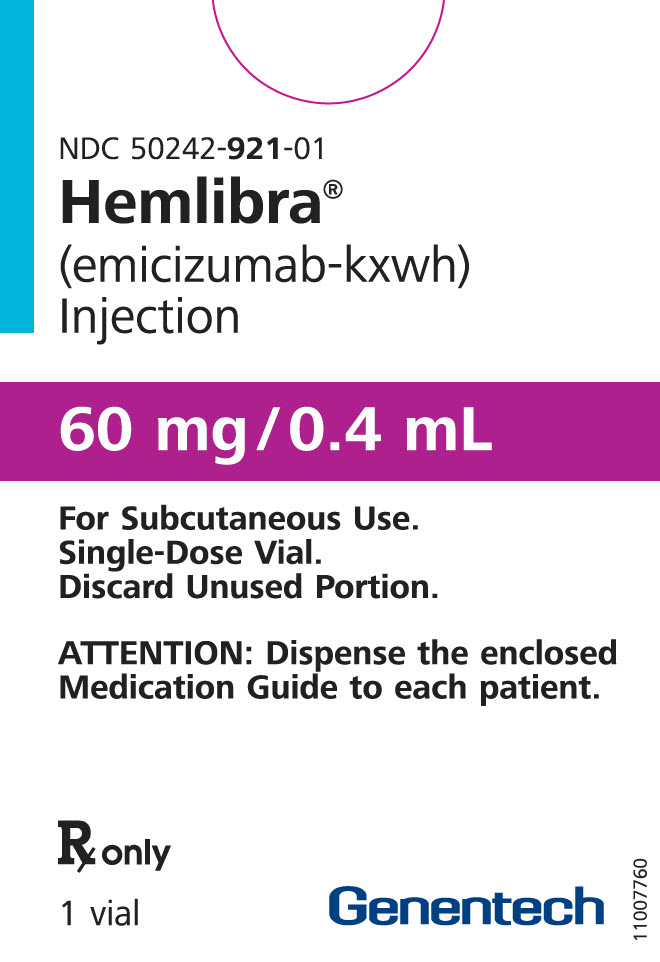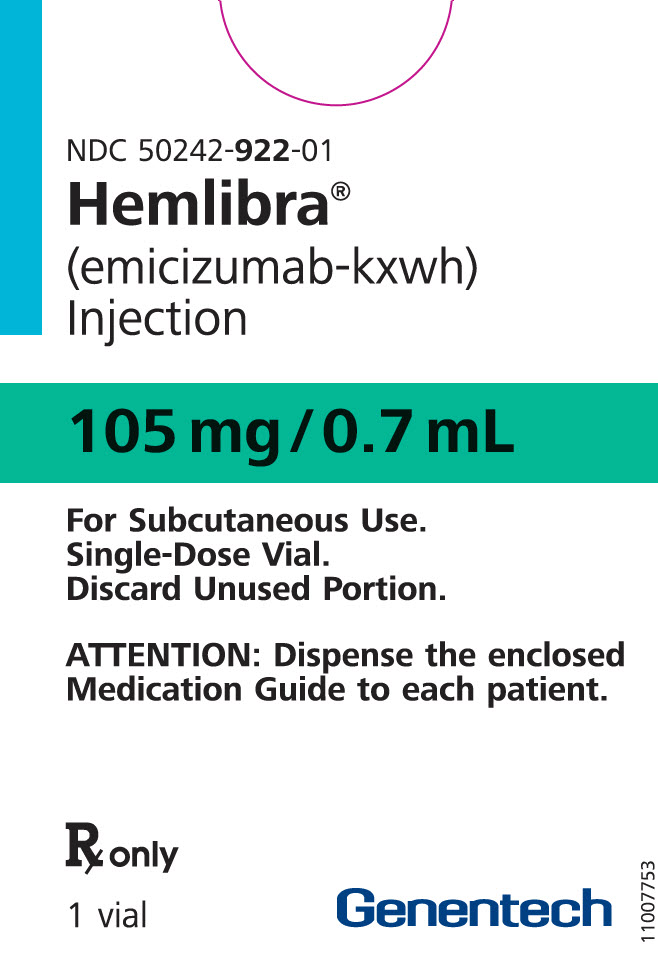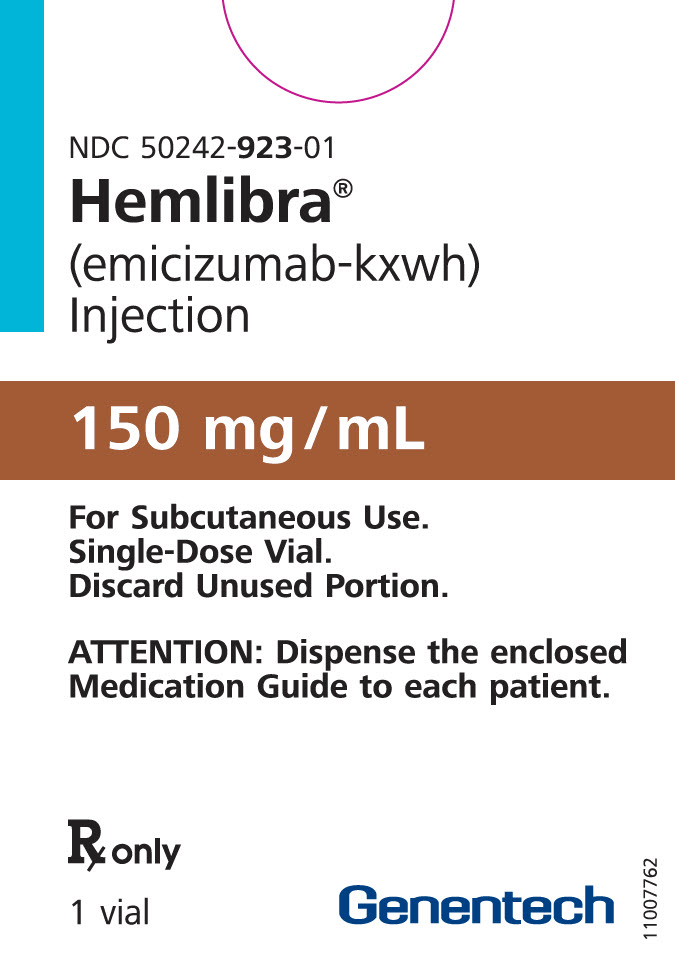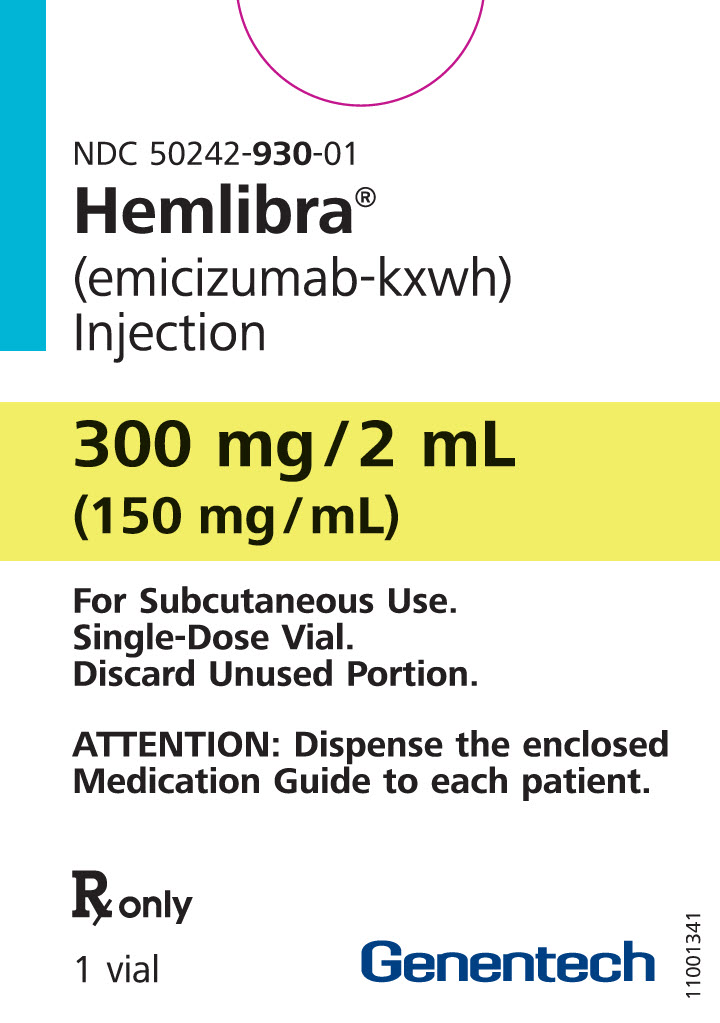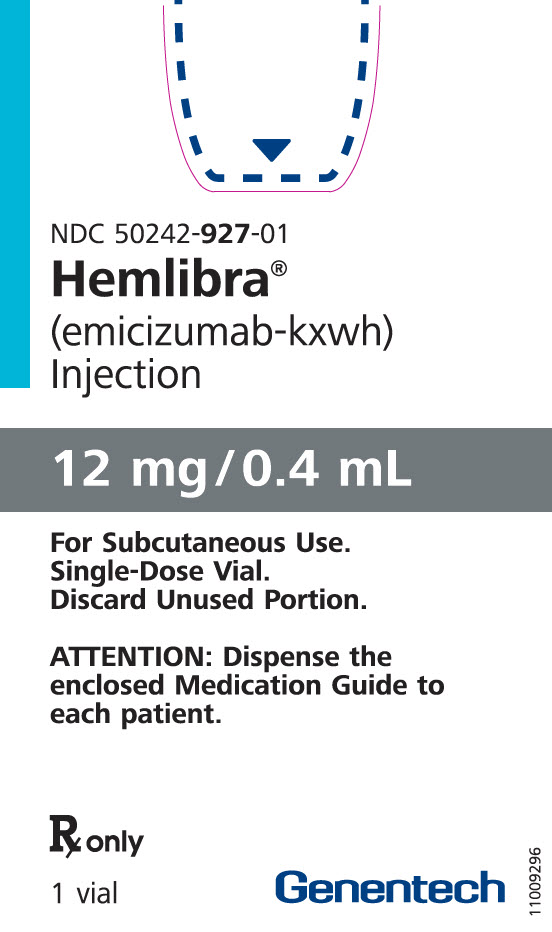 DRUG LABEL: Hemlibra
NDC: 50242-920 | Form: INJECTION, SOLUTION
Manufacturer: Genentech, Inc.
Category: prescription | Type: HUMAN PRESCRIPTION DRUG LABEL
Date: 20250711

ACTIVE INGREDIENTS: EMICIZUMAB 30 mg/1 mL
INACTIVE INGREDIENTS: HISTIDINE; ASPARTIC ACID; ARGININE; POLOXAMER 188; WATER

HIGHLIGHTS OF PRESCRIBING INFORMATION

These highlights do not include all the information needed to use HEMLIBRA safely and effectively. See full prescribing information for HEMLIBRA.
HEMLIBRA® (emicizumab-kxwh) injection, for subcutaneous use
Initial U.S. Approval: 2017

WARNING: THROMBOTIC MICROANGIOPATHY AND THROMBOEMBOLISM

See full prescribing information for complete boxed warning.

Cases of thrombotic microangiopathy and thrombotic events were reported when on average a cumulative amount of >100 U/kg/24 hours of activated prothrombin complex concentrate (aPCC) was administered for 24 hours or more to patients receiving HEMLIBRA prophylaxis. Monitor for the development of thrombotic microangiopathy and thrombotic events if aPCC is administered. Discontinue aPCC and suspend dosing of HEMLIBRA if symptoms occur.

1 INDICATIONS AND USAGE

HEMLIBRA is a bispecific factor IXa- and factor X-directed antibody indicated for routine prophylaxis to prevent or reduce the frequency of bleeding episodes in adult and pediatric patients ages newborn and older with hemophilia A (congenital factor VIII deficiency) with or without factor VIII inhibitors. (1)

2 DOSAGE AND ADMINISTRATION

Recommended loading dose is 3 mg/kg by subcutaneous injection once weekly for the first 4 weeks, followed by a maintenance dose of:

- 1.5 mg/kg once every week, or
- 3 mg/kg once every two weeks, or
- 6 mg/kg once every four weeks. (2.1)

See Full Prescribing Information for important preparation and administration instructions. (2.2)

3 DOSAGE FORMS AND STRENGTHS

Injection:

- 12 mg/0.4 mL in a single-dose vial (3)
- 30 mg/mL in a single-dose vial (3)
- 60 mg/0.4 mL in a single-dose vial (3)
- 105 mg/0.7 mL in a single-dose vial (3)
- 150 mg/mL in a single-dose vial (3)
- 300 mg/2 mL (150 mg/mL) in a single-dose vial (3)

4 CONTRAINDICATIONS

None (4)

5 WARNINGS AND PRECAUTIONS

- Immunogenicity: Anti-emicizumab antibodies (including neutralizing antibodies) have developed in HEMLIBRA-treated patients.
- In case of clinical signs of loss of efficacy, promptly assess the etiology and consider a change in treatment if neutralizing antibodies are suspected. (5.3, 12.6, 14.3)
- Laboratory Coagulation Test Interference: HEMLIBRA interferes with activated clotting time (ACT), activated partial thromboplastin time (aPTT), and coagulation laboratory tests based on aPTT, including one-stage aPTT-based single-factor assays, aPTT-based Activated Protein C Resistance (APC-R), and Bethesda assays (clotting-based) for factor VIII (FVIII) inhibitor titers. Intrinsic pathway clotting-based laboratory tests should not be used. (5.4, 7.2)

6 ADVERSE REACTIONS

Most common adverse reactions (incidence ≥ 10%) are injection site reactions, headache, and arthralgia. (6.1)

To report SUSPECTED ADVERSE REACTIONS, contact Genentech at 1-888-835-2555 or FDA at 1-800-FDA-1088 or www.fda.gov/medwatch.

FULL PRESCRIBING INFORMATION

WARNING: THROMBOTIC MICROANGIOPATHY AND THROMBOEMBOLISM

Cases of thrombotic microangiopathy and thrombotic events were reported when on average a cumulative amount of >100 U/kg/24 hours of activated prothrombin complex concentrate was administered for 24 hours or more to patients receiving HEMLIBRA prophylaxis. Monitor for the development of thrombotic microangiopathy and thrombotic events if aPCC is administered. Discontinue aPCC and suspend dosing of HEMLIBRA if symptoms occur.

1 INDICATIONS AND USAGE

HEMLIBRA is indicated for routine prophylaxis to prevent or reduce the frequency of bleeding episodes in adult and pediatric patients ages newborn and older with hemophilia A (congenital factor VIII deficiency) with or without factor VIII inhibitors.

2 DOSAGE AND ADMINISTRATION

2.1 Recommended Dosage

For subcutaneous use only.

The recommended loading dose is 3 mg/kg by subcutaneous injection once weekly for the first 4 weeks, followed by a maintenance dose of:

- 1.5 mg/kg once every week, or
- 3 mg/kg once every two weeks, or
- 6 mg/kg once every four weeks.

The selection of a maintenance dose should be based on healthcare provider preference with consideration of regimens that may increase patient adherence.

Discontinue the prophylactic use of bypassing agents the day before starting HEMLIBRA prophylaxis.

The prophylactic use of factor VIII (FVIII) products may be continued during the first week of HEMLIBRA prophylaxis.

Missed Dose

If a dose of HEMLIBRA is missed administer as soon as possible and then resume usual dosing schedule. Do not administer two doses on the same day to make up for a missed dose.

2.2 Preparation and Administration

HEMLIBRA is intended for use under the guidance of a healthcare provider. After proper training in subcutaneous injection technique, a patient may self-inject, or the patient's caregiver may administer HEMLIBRA, if a healthcare provider determines that it is appropriate. Self-administration is not recommended for children less than 7 years of age. The HEMLIBRA "Instructions for Use" contains more detailed instructions on the preparation and administration of HEMLIBRA [see Instructions for Use].

- Visually inspect HEMLIBRA for particulate matter and discoloration before administration. HEMLIBRA for subcutaneous administration is a colorless to slightly yellow solution. Do not use if particulate matter is visible or product is discolored.
- A syringe, a transfer needle with filter and an injection needle are needed to withdraw HEMLIBRA solution from the vial and inject it subcutaneously.
- Refer to the HEMLIBRA "Instructions for Use" for handling instructions when combining vials. Do not combine HEMLIBRA vials of different concentrations (i.e. 30 mg/mL and 150 mg/mL) in a single injection.

Please see below the selection criteria for the recommended device options:

- Administer doses of HEMLIBRA up to 1 mL with a 1 mL syringe. A 1 mL syringe fulfilling the following criteria may be used: Transparent polypropylene or polycarbonate syringe with Luer-Lock tip, graduation 0.01 mL, sterile, for injection only, single-use, latex-free and non-pyrogenic, commercially available in the US.
- Administer doses of HEMLIBRA greater than 1 mL and up to 2 mL with a 2 mL or 3 mL syringe. A 2 mL or 3 mL syringe fulfilling the following criteria may be used: Transparent polypropylene or polycarbonate syringe with Luer-Lock tip, graduation 0.1 mL, sterile, for injection only, single-use, latex-free, and non-pyrogenic, commercially available in the US.
- A transfer needle with a filter fulfilling the following criteria should be used: Stainless steel needle with Luer-Lock connection, sterile, 18 gauge, length 1 to 1½ inch, single bevel or semi-blunted tip, single-use, latex-free, containing a 5-micron filter and non-pyrogenic, commercially available in the US.
- An injection needle fulfilling the following criteria may be used: Stainless steel with Luer-Lock connection, sterile, 26 gauge (acceptable range: 25 – 27 gauge), length preferably ⅜ inch or maximal length ½ inch, single-use, latex-free and non-pyrogenic, including needle safety feature, commercially available in the US.
- Administer each injection at a different anatomic location (upper outer arms, thighs, or any quadrant of abdomen) than the previous injection. An injection should never be given into moles, scars, or areas where the skin is tender, bruised, red, hard, or not intact. Administration of HEMLIBRA in the upper outer arm should only be performed by a caregiver or healthcare provider.
- Discard any unused HEMLIBRA remaining in the single-dose vial.

3 DOSAGE FORMS AND STRENGTHS

HEMLIBRA is available as a colorless to slightly yellow solution in single-dose vials.

Injection:

- 12 mg/0.4 mL
- 30 mg/mL
- 60 mg/0.4 mL
- 105 mg/0.7 mL
- 150 mg/mL
- 300 mg/2 mL (150 mg/mL)

4 CONTRAINDICATIONS

None.

5 WARNINGS AND PRECAUTIONS

5.1 Thrombotic Microangiopathy Associated with HEMLIBRA and aPCC

Cases of thrombotic microangiopathy (TMA) were reported from clinical trials when on average a cumulative amount of >100 U/kg/24 hours of activated prothrombin complex concentrate (aPCC) was administered for 24 hours or more to patients receiving HEMLIBRA prophylaxis. In clinical trials, thrombotic microangiopathy was reported in 0.8% of patients (3/391) and in 8.1% of patients (3/37) who received at least one dose of aPCC. Patients presented with thrombocytopenia, microangiopathic hemolytic anemia, and acute kidney injury, without severe deficiencies in ADAMTS13 activity.

Evidence of improvement was seen within one week following discontinuation of aPCC. One patient resumed HEMLIBRA following resolution of TMA.

Consider the benefits and risks if aPCC must be used in a patient receiving HEMLIBRA prophylaxis. Due to the long half-life of HEMLIBRA, the potential for an interaction with aPCC may persist for up to 6 months after the last dose. Monitor for the development of TMA when administering aPCC. Immediately discontinue aPCC and interrupt HEMLIBRA prophylaxis if clinical symptoms and/or laboratory findings consistent with TMA occur, and manage as clinically indicated. Consider the benefits and risks of resuming HEMLIBRA prophylaxis following complete resolution of TMA on a case-by-case basis.

5.2 Thromboembolism Associated with HEMLIBRA and aPCC

Thrombotic events were reported from clinical trials when on average a cumulative amount of >100 U/kg/24 hours of aPCC was administered for 24 hours or more to patients receiving HEMLIBRA prophylaxis. In clinical trials, thrombotic events were reported in 0.5% of patients (2/391) and in 5.4% of patients (2/37) who received at least one dose of aPCC.

No thrombotic event required anticoagulation therapy. Evidence of improvement or resolution was seen within one month following discontinuation of aPCC. One patient resumed HEMLIBRA following resolution of thrombotic event.

Consider the benefits and risks if aPCC must be used in a patient receiving HEMLIBRA prophylaxis. Due to the long half-life of HEMLIBRA, the potential for an interaction with aPCC may persist for up to 6 months after the last dose. Monitor for the development of thromboembolism when administering aPCC. Immediately discontinue aPCC and interrupt HEMLIBRA prophylaxis if clinical symptoms, imaging, or laboratory findings consistent with thromboembolism occur, and manage as clinically indicated. Consider the benefits and risks of resuming HEMLIBRA prophylaxis following complete resolution of thrombotic events on a case-by-case basis.

5.3 Immunogenicity

Treatment with HEMLIBRA may induce anti-drug antibodies. Anti-emicizumab-kxwh antibodies were reported in 5.1% of patients (34/668) treated with HEMLIBRA in clinical trials. Most patients with anti-emicizumab-kxwh antibodies did not experience a change in HEMLIBRA plasma concentrations or an increase in bleeding events; however, in uncommon cases (incidence < 1%), the presence of neutralizing antibodies with decreasing plasma concentration may be associated with loss of efficacy [see Clinical Pharmacology (12.6), Clinical Studies (14.3)].

Monitor for clinical signs of loss of efficacy (e.g., increase in breakthrough bleeding events) and if observed, promptly assess the etiology and consider a change in treatment if neutralizing anti-emicizumab-kxwh antibodies are suspected.

5.4 Laboratory Coagulation Test Interference

HEMLIBRA affects intrinsic pathway clotting-based laboratory tests, including activated clotting time (ACT), activated partial thromboplastin time (aPTT), and all assays based on aPTT, such as one-stage factor VIII (FVIII) activity (Table 1). Therefore, intrinsic pathway clotting-based laboratory test results in patients treated with HEMLIBRA should not be used to monitor HEMLIBRA activity, determine dosing for factor replacement or anti-coagulation, or measure FVIII inhibitor titers [see Drug Interactions (7.2)]. Laboratory tests affected and unaffected by HEMLIBRA are shown in Table 1.

Table 1 Coagulation Test Results Affected and Unaffected by HEMLIBRA
Results Affected by HEMLIBRA | Results Unaffected by HEMLIBRA
Activated partial thromboplastin time (aPTT) Bethesda assays (clotting-based) for FVIII inhibitor titers One-stage, aPTT-based, single-factor assays aPTT-based Activated Protein C Resistance (APC-R) Activated clotting time (ACT) | Bethesda assays (bovine chromogenic) for FVIII inhibitor titers Thrombin time (TT) One-stage, prothrombin time (PT)-based, single-factor assays Chromogenic-based single-factor assays other than FVIII [For important considerations regarding FVIII chromogenic activity assays, see Drug Interactions (7.2).] Immuno-based assays (i.e., ELISA, turbidimetric methods) Genetic tests of coagulation factors (e.g., Factor V Leiden, Prothrombin 20210)

6 ADVERSE REACTIONS

The following serious adverse reactions are described elsewhere in the labeling:

- Thrombotic Microangiopathy Associated with HEMLIBRA and aPCC [see Warnings and Precautions (5.1)]
- Thromboembolism Associated with HEMLIBRA and aPCC [see Warnings and Precautions (5.2)]

6.1 Clinical Trials Experience

Because clinical trials are conducted under widely varying conditions, adverse reaction rates observed in the clinical trials of a drug cannot be directly compared to rates in the clinical trials of another drug and may not reflect the rates observed in practice.

The following adverse reactions are based on pooled data from two randomized trials in adult and adolescent patients (HAVEN 1 and HAVEN 3), one single-arm trial in adult and adolescent patients (HAVEN 4), one single-arm trial in pediatric patients (HAVEN 2), and one dose-finding trial, in which a total of 391 male patients with hemophilia A received at least one dose of HEMLIBRA as routine prophylaxis. Two hundred eighty-one patients (72%) were adults (18 years and older), 50 (13%) were adolescents (12 years up to less than 18 years), 55 (14%) were children (2 years up to less than 12 years), and five (1%) were infants (1 month up to less than 2 years). The median duration of exposure across the studies was 34.1 weeks (0.1 to 224.4 weeks).

The most frequently reported adverse reactions observed in ≥ 10% of patients treated with HEMLIBRA were injection site reactions, headache, and arthralgia.

Four patients (1%) in the clinical trials receiving HEMLIBRA prophylaxis withdrew from treatment due to adverse reactions, which were thrombotic microangiopathy, skin necrosis and superficial thrombophlebitis, headache, and injection site reaction.

Adverse reactions observed in patients who received HEMLIBRA are shown in Table 2.

Table 2 Adverse Reactions Reported in ≥ 5% of Patients from Pooled Clinical Trials with HEMLIBRA
Body System | Adverse Reaction | Number of Patients n (%) (N = 391)
General Disorders and Administration Site Conditions | Injection site reaction [Includes injection site bruising, injection site discomfort, injection site erythema, injection site hematoma, injection site induration, injection site pain, injection site pruritus, injection site rash, injection site reaction, injection site swelling, injection site urticaria, and injection site warmth.] | 85 (22%)
General Disorders and Administration Site Conditions | Pyrexia | 23 (6%)
Nervous System Disorders | Headache | 57 (15%)
Gastrointestinal Disorders | Diarrhea | 22 (6%)
Musculoskeletal and Connective Tissue Disorders | Arthralgia | 59 (15%)

Characterization of aPCC treatment in pooled clinical trials

There were 130 instances of aPCC treatment in 37 patients, of which 13 instances (10%) consisted of on average a cumulative amount of >100 U/kg/24 hours of aPCC for 24 hours or more; two of the 13 were associated with thrombotic events and three of the 13 were associated with TMA (Table 3). No TMA or thrombotic events were associated with the remaining instances of aPCC treatment.

Table 3 Characterization of aPCC Treatment [An instance of aPCC treatment is defined as all doses of aPCC received by a patient, for any reason, until there was a 36-hour treatment-free break.] in Pooled Clinical Trials
Duration of aPCC treatment | Average cumulative amount of aPCC over 24 hours (U/kg/24 hours)
Duration of aPCC treatment | < 50 | 50 – 100 | > 100
< 24 hours | 11 | 76 | 18
24 – 48 hours | 0 | 6 | 3 [Thrombotic event.]
> 48 hours | 1 | 5 | 10, [Thrombotic microangiopathy.] ,,

Injection Site Reactions

In total, 85 patients (22%) reported injection site reactions (ISRs). All ISRs observed in HEMLIBRA clinical trials were reported as mild to moderate intensity and 93% resolved without treatment. The commonly reported ISR symptoms were injection site erythema (11%), injection site pain (4%), and injection site pruritus (4%).

Other Less Common (<1%) Reactions

- Rhabdomyolysis

Rhabdomyolysis was reported in two adult patients with asymptomatic elevations in serum creatine kinase without associated renal or musculoskeletal symptoms. In both instances, the event occurred following an increase in physical activity.

6.2 Postmarketing Experience

The following adverse reactions have been identified during post-approval use of HEMLIBRA. Because these reactions are reported voluntarily from a population of uncertain size, it is not always possible to reliably estimate their frequency or establish a causal relationship to drug exposure.

Skin and subcutaneous tissue disorders: rash, urticaria, angioedema.

Immune system disorders: hypersensitivity.

7 DRUG INTERACTIONS

7.1 Hypercoagulability with Concomitant Use of aPCC

Clinical experience suggests that a drug interaction exists with HEMLIBRA and aPCC [see Warnings and Precautions (5.1, 5.2)].

7.2 Drug-Laboratory Test Interactions

HEMLIBRA restores the tenase cofactor activity of missing activated factor VIII (FVIIIa). Coagulation laboratory tests based on intrinsic clotting (i.e., aPTT) measure the total clotting time including time needed for activation of FVIII to FVIIIa by thrombin. Such intrinsic pathway-based tests will yield overly shortened clotting times with HEMLIBRA, which does not require activation by thrombin. The overly shortened intrinsic clotting time will then disturb all single-factor assays based on aPTT, such as the one-stage FVIII activity assay; however, single-factor assays utilizing chromogenic or immuno-based methods are unaffected by HEMLIBRA and may be used to monitor coagulation parameters during treatment, with specific considerations for FVIII chromogenic activity assays as described below.

Chromogenic FVIII activity tests may be manufactured with either human or bovine coagulation proteins. Assays containing human coagulation factors are responsive to HEMLIBRA but may overestimate the clinical hemostatic potential of HEMLIBRA. In contrast, assays containing bovine coagulation factors are insensitive to HEMLIBRA (no activity measured) and can be used to monitor endogenous or infused FVIII activity, or to measure anti-FVIII inhibitors.

HEMLIBRA remains active in the presence of inhibitors against FVIII, so it will produce a false-negative result in clotting-based Bethesda assays for functional inhibition of FVIII. Instead, a chromogenic Bethesda assay utilizing a bovine-based FVIII chromogenic test that is insensitive to HEMLIBRA may be used.

Due to the long half-life of HEMLIBRA, effects on coagulation assays may persist for up to 6 months after the last dose [see Clinical Pharmacology (12.3)].

8 USE IN SPECIFIC POPULATIONS

8.1 Pregnancy

Risk Summary

There are no available data on HEMLIBRA use in pregnant women to inform a drug-associated risk of major birth defects and miscarriage. Animal reproduction studies have not been conducted with emicizumab-kxwh. It is not known whether HEMLIBRA can cause fetal harm when administered to a pregnant woman or can affect reproduction capacity. HEMLIBRA should be used during pregnancy only if the potential benefit for the mother outweighs the risk to the fetus.

All pregnancies have a background risk of birth defect, loss, or other adverse outcomes. The estimated background risk of major birth defects and miscarriage for the indicated populations is unknown. In the U.S. general population, the estimated background risk of major birth defect and miscarriage in clinically recognized pregnancies is 2 – 4% and 15 – 20%, respectively.

8.2 Lactation

Risk Summary

There is no information regarding the presence of emicizumab-kxwh in human milk, the effects on the breastfed child, or the effects on milk production. Human IgG is known to be present in human milk. The developmental and health benefits of breastfeeding should be considered along with the mother's clinical need for HEMLIBRA and any potential adverse effects on the breastfed child from HEMLIBRA or from the underlying maternal condition.

8.3 Females and Males of Reproductive Potential

Contraception

Women of childbearing potential should use contraception while receiving HEMLIBRA.

8.4 Pediatric Use

The safety and efficacy of HEMLIBRA have been established in pediatric patients. Use of HEMLIBRA in pediatric patients with hemophilia A is supported by two randomized trials (HAVEN 1 and HAVEN 3) and two single-arm trials (HAVEN 2 and HAVEN 4). All clinical trials included pediatric patients in the following age group: 47 adolescents (12 years up to less than 18 years). Only HAVEN 2 included pediatric patients in the following age groups: 55 children (2 years up to less than 12 years) and five infants (1 month up to less than 2 years). No differences in efficacy were observed between the different age groups [see Clinical Studies (14)].

The steady-state plasma trough concentrations of emicizumab-kxwh were comparable in adult and pediatric patients older than 6 months at equivalent weight-based doses. Lower concentrations of emicizumab-kxwh were predicted in pediatric patients less than 6 months old [see Clinical Pharmacology (12.3)].

In general, the adverse reactions in HEMLIBRA-treated pediatric patients were similar in type to those seen in adult patients with hemophilia A [see Adverse Reactions (6.1)].

8.5 Geriatric Use

Clinical studies of HEMLIBRA did not include a sufficient number of patients aged 65 and over to determine whether they respond differently from younger patients. Other reported clinical experience has not identified differences in responses between the elderly and younger patients.

11 DESCRIPTION

Emicizumab-kxwh is a humanized monoclonal modified immunoglobulin G4 (IgG4) bispecific antibody binding factor IXa and factor X. Emicizumab-kxwh has an approximate molecular weight of 145.6 kDa and is produced in genetically engineered mammalian (Chinese hamster ovary) cells. Emicizumab-kxwh has no structural relationship or sequence homology to FVIII and, as such, does not induce or enhance the development of direct inhibitors to FVIII.

HEMLIBRA (emicizumab-kxwh) injection is a sterile, preservative-free, colorless to slightly yellow solution for subcutaneous injection supplied in single-dose vials containing emicizumab-kxwh at 12 mg/0.4 mL, 30 mg/mL, 60 mg/0.4 mL, 105 mg/0.7 mL, 150 mg/mL, or 300 mg/2 mL.

Each single-dose 12 mg vial contains a 0.4 mL solution of emicizumab-kxwh (12 mg), L-arginine (10.5 mg), L-histidine (1.2 mg), and poloxamer 188 (0.2 mg), adjusted to pH 6.0 with L-aspartic acid.

Each single-dose 30 mg vial contains a 1 mL solution of emicizumab-kxwh (30 mg), L-arginine (26.1 mg), L-histidine (3.1 mg), and poloxamer 188 (0.5 mg), adjusted to pH 6.0 with L-aspartic acid.

Each single-dose 60 mg vial contains a 0.4 mL solution of emicizumab-kxwh (60 mg), L-arginine (10.5 mg), L-histidine (1.2 mg), and poloxamer 188 (0.2 mg), adjusted to pH 6.0 with L-aspartic acid.

Each single-dose 105 mg vial contains a 0.7 mL solution of emicizumab-kxwh (105 mg), L-arginine (18.3 mg), L-histidine (2.2 mg), and poloxamer 188 (0.4 mg), adjusted to pH 6.0 with L-aspartic acid.

Each single-dose 150 mg vial contains a 1 mL solution of emicizumab-kxwh (150 mg), L-arginine (26.1 mg), L-histidine (3.1 mg), and poloxamer 188 (0.5 mg), adjusted to pH 6.0 with L-aspartic acid.

Each single-dose 300 mg vial contains a 2 mL solution of emicizumab-kxwh (300 mg), L-arginine (52.3 mg), L-histidine (6.2 mg), and poloxamer 188 (1 mg), adjusted to pH 6.0 with L-aspartic acid.

12 CLINICAL PHARMACOLOGY

12.1 Mechanism of Action

HEMLIBRA bridges activated factor IX and factor X to restore the function of missing activated factor VIII that is needed for effective hemostasis.

12.3 Pharmacokinetics

Emicizumab-kxwh exhibited dose-proportional pharmacokinetics over a dose range of 0.3 mg/kg (0.1 times approved recommended starting dosage) to 6 mg/kg following subcutaneous administration. Following multiple subcutaneous administrations of a loading dose of 3 mg/kg emicizumab-kxwh once weekly for the first 4 weeks in hemophilia A patients, mean (± SD) trough plasma concentrations of 52.6 ± 13.6 μg/mL was achieved at Week 5. Sustained mean (± SD) plasma concentrations of emicizumab-kxwh at steady-state with the recommended maintenance doses are shown in Table 4.

Table 4 Mean (± SD) Steady-State Concentrations after emicizumab-kxwh Loading Dose by Maintenance Dose Regimen
 | Maintenance Dose
Parameters | 1.5 mg/kg once every week | 3 mg/kg once every two weeks | 6 mg/kg once every four weeks
Cmax, ss (µg/mL) | 55.1 ± 15.9 | 58.3 ± 16.4 | 67 ± 17.7
AUCss,τ (µg/mL*day) | 376 ± 109 | 752 ± 218 | 1503 ± 437
Ctrough, ss (µg/mL) | 51.2± 15.2 | 46.9 ± 14.8 | 38.5 ± 14.2
Cmax/ Ctrough ratio (µg/mL) | 1.08 ± 0.03 | 1.26 ± 0.12 | 1.85 ± 0.47
AUCss,τ = area under the concentration time curve at steady-state over the dosing interval (τ = 1, 2, or 4 weeks); Cmax, ss = maximum plasma concentration at steady state; Ctrough, ss = trough concentration at steady state.

Absorption

Following subcutaneous administration, the mean (± SD) absorption half-life was 1.6 ± 1 day.

The absolute bioavailability following subcutaneous administration of 1 mg/kg was between 80.4% and 93.1%. Similar pharmacokinetic profiles were observed following subcutaneous administration in the abdomen, upper arm, and thigh [see Dosage and Administration (2.2)].

Distribution

The mean apparent volume of distribution (% coefficient of variation [%CV]) was 10.4 L (26.0%).

Elimination

The mean apparent clearance (%CV) was 0.27 L/day (28.4%) and the mean elimination apparent half-life (± SD) was 26.9 ± 9.1 days.

Specific Populations

The pharmacokinetics of emicizumab-kxwh are not influenced by age (1 year to 77 years), race (White 62.7%, Asian 22.9%, and Black 8%), inhibitor status (inhibitor present, 50%), mild hepatic impairment (defined as total bilirubin 1× to ≤1.5× the upper limit of normal (ULN) and any aspartate transaminase (AST) level), moderate hepatic impairment (defined as total bilirubin 1.5× to ≤3× the ULN and any AST level), mild renal impairment (defined as creatinine clearance (CrCl) of 60 – 89 mL/min), and moderate renal impairment (defined as CrCl of 30 – 59 mL/min). Emicizumab-kxwh has not been studied in patients with severe hepatic or renal impairment.

In pediatric patients less than 6 months old, the predicted concentrations of emicizumab-kxwh were 19% to 33% lower than the older patients, especially with the 3 mg/kg once every two weeks or 6 mg/kg once every four weeks maintenance dose.

Body weight: The apparent clearance and volume of distribution of emicizumab-kxwh increased with increasing body weight (9 kg to 156 kg). Dosing in mg/kg provides similar emicizumab-kxwh exposure across body weight range.

Drug Interaction Studies

No drug-drug interaction studies have been conducted with HEMLIBRA.

12.6 Immunogenicity

The observed incidence of anti-drug antibodies is highly dependent on the sensitivity and specificity of the assay. Differences in assay methods preclude meaningful comparisons of the incidence of anti-drug antibodies in the studies described below with the incidence of anti-drug antibodies in other studies, including those of HEMLIBRA or of other emicizumab products.

In the clinical trials with HEMLIBRA, 5.1% of patients (34/668) tested positive for anti-emicizumab-kxwh antibodies. Participants were exposed to emicizumab-kxwh for a median interquartile range (IQR) of 103.1 (82.4 – 148.1) weeks. Samples testing for anti-drug antibodies were obtained at baseline and at trough periodically throughout the studies duration.

Anti-Drug Antibody Effects on Pharmacokinetics

Antibody positive samples were further evaluated for neutralizing anti-emicizumab-kxwh antibodies using a modified FVIII chromogenic assay. A total of 668 patients were tested for anti-emicizumab-kxwh antibodies. 5.1% of patients (34/668) tested positive for anti-emicizumab-kxwh antibodies and 2.7% of patients (18/668) developed anti-emicizumab-kxwh antibodies that were neutralizing in vitro. Of these, 2.7% of patients (18/668), the neutralizing anti-emicizumab-kxwh antibodies did not have a clinically meaningful impact on the pharmacokinetics of HEMLIBRA in 2.1% of patients (14/668), while decreased emicizumab-kxwh plasma concentrations were observed in 0.6% of patients (4/668).

Anti-Drug Antibody Effects on Pharmacodynamics

One patient (1/668; 0.1%) developed neutralizing anti-emicizumab-kxwh antibodies and had decreased emicizumab-kxwh plasma concentrations, and experienced loss of efficacy (manifest as breakthrough bleeding) after 5 weeks of treatment and discontinued HEMLIBRA treatment. [see Warnings and Precautions (5.3), Clinical Studies (14.3)].

13 NONCLINICAL TOXICOLOGY

13.1 Carcinogenesis, Mutagenesis, Impairment of Fertility

Studies in animals investigating the carcinogenic effects of emicizumab-kxwh have not been conducted. In vitro and in vivo testing of emicizumab-kxwh for genotoxicity was not conducted.

Animal fertility studies have not been conducted; however, emicizumab-kxwh did not cause any toxicological changes in the reproductive organs of male or female cynomolgus monkeys at doses of up to 30 mg/kg/week in subcutaneous general toxicity studies of up to 26-week duration and at doses of up to 100 mg/kg/week in a 4-week intravenous general toxicity study.

14 CLINICAL STUDIES

14.1 Hemophilia A without FVIII Inhibitors

The efficacy of HEMLIBRA for routine prophylaxis in patients with hemophilia A without FVIII inhibitors was evaluated in two clinical trials [adult and adolescent studies (HAVEN 3 and HAVEN 4)].

HAVEN 3 (Adult and Adolescent Patients)

The HAVEN 3 study (NCT02847637) was a randomized, multicenter, open-label, clinical trial in 152 adult and adolescent males (aged ≥ 12 years and ≥ 40 kg) with hemophilia A without FVIII inhibitors who previously received either episodic (on demand) or prophylactic treatment with FVIII. Patients received HEMLIBRA prophylaxis, 3 mg/kg once weekly for the first 4 weeks followed by either 1.5 mg/kg once every week [Arms A and D] or 3 mg/kg once every two weeks [Arm B] thereafter, or no prophylaxis (Arm C). Patients in Arm C could switch to HEMLIBRA prophylaxis (3 mg/kg once every two weeks) after completing at least 24 weeks without prophylaxis. For Arms A and B, dose up-titration to 3 mg/kg once every week was allowed after 24 weeks on HEMLIBRA prophylaxis for patients who experienced two or more qualified bleeds (i.e., spontaneous and clinically significant bleeds occurring at steady state). For Arm D patients, dose up-titration was allowed after the second qualifying bleed. During the study, five patients underwent up-titration of their maintenance dose; however, this study was not designed to investigate the 3 mg/kg once every week dosing regimen.

Eighty-nine patients previously treated with episodic (on demand) FVIII were randomized in a 2:2:1 ratio to receive HEMLIBRA prophylaxis 1.5 mg/kg once every week (Arm A), 3 mg/kg once every two weeks (Arm B), or no prophylaxis (Arm C), with stratification by prior 24-week bleed rate (< 9 or ≥ 9). Sixty-three patients previously treated with prophylactic FVIII were enrolled into Arm D to receive HEMLIBRA prophylaxis (1.5 mg/kg once every week).

Efficacy was evaluated after a minimum of 24 weeks of follow-up based on the bleed rate for bleeds requiring treatment with coagulation factors among patients previously treated with episodic (on-demand) FVIII who were randomized to HEMLIBRA prophylaxis 1.5 mg/kg once every week (Arm A) or 3 mg/kg once every two weeks (Arm B) compared with those receiving no prophylaxis (Arm C). The study also evaluated the randomized comparison of Arms A and C and Arms B and C for the efficacy of HEMLIBRA prophylaxis in reducing the number of all bleeds, spontaneous bleeds, joint bleeds, and target joint bleeds.

The efficacy of HEMLIBRA prophylaxis compared with previous prophylactic FVIII was also evaluated in patients who had participated in a non-interventional study (NIS) prior to enrollment (Arm D). Only patients from the NIS were included in this comparison, because bleed and treatment data were collected with the same level of granularity as that used in HAVEN 3.

The efficacy results of HEMLIBRA prophylaxis (1.5 mg/kg once every week and 3 mg/kg once every two weeks) compared with no prophylaxis with respect to rate of treated bleeds, all bleeds, treated spontaneous bleeds, treated joint bleeds, and treated target joint bleeds are shown in Table 5.

Table 5 Annualized Bleed Rate with HEMLIBRA Prophylaxis versus No Prophylaxis in Patients ≥ 12 Years of Age without Factor VIII Inhibitors
Endpoint | HEMLIBRA 1.5 mg/kg once every week (N = 36) | HEMLIBRA 3 mg/kg once every two weeks (N = 35) | No Prophylaxis (N = 18)
Treated Bleeds
ABR (95% CI) [Based on negative binomial regression model.] | 1.5 (0.9, 2.5) | 1.3 (0.8, 2.3) | 38.2 (22.9, 63.8)
% reduction (95% CI) p-value | 96% (92.5%, 98%) < 0.0001 | 97% (93.4%, 98.3%) < 0.0001 | -
% patients with 0 bleeds (95% CI) | 55.6 (38.1, 72.1) | 60 (42.1, 76.1) | 0 (0, 18.5)
Median ABR (IQR) | 0 (0, 2.5) | 0 (0, 1.9) | 40.4 (25.3, 56.7)
All Bleeds
ABR (95% CI) | 2.5 (1.6, 3.9) | 2.6 (1.6, 4.3) | 47.6 (28.5, 79.6)
% reduction (95% CI) p-value | 95% (90.1%, 97%) < 0.0001 | 94% (89.7%, 97%) < 0.0001 | -
% patients with 0 bleeds (95% CI) | 50 (32.9, 67.1) | 40 (23.9, 57.9) | 0 (0, 18.5)
Median ABR (IQR) | 0.6 (0, 3.9) | 1.6 (0, 4) | 46.9 (26.1, 73.9)
Treated Spontaneous Bleeds
ABR (95% CI) | 1.0 (0.5, 1.9) | 0.3 (0.1, 0.8) | 15.6 (7.6, 31.9)
% reduction (95% CI) p-value | 94% (84.9%, 97.5%) < 0.0001 | 98% (94.4%, 99.4%) < 0.0001 | -
% patients with 0 bleeds (95% CI) | 66.7 (49.0, 81.4) | 88.6 (73.3, 96.8) | 22.2 (6.4, 47.6)
Median ABR (IQR) | 0 (0, 1.3) | 0 (0, 0) | 10.8 (2.1, 26)
Treated Joint Bleeds
ABR (95% CI) | 1.1 (0.6, 1.9) | 0.9 (0.4, 1.7) | 26.5 (14.7, 47.8)
% reduction (95% CI) p-value | 96% (91.5%, 98.1%) < 0.0001 | 97% (93%, 98.5%) < 0.0001 | -
% patients with 0 bleeds (95% CI) | 58.3 (40.8, 74.5) | 74.3 (56.7, 87.5) | 0 (0, 18.5)
Median ABR (IQR) | 0 (0, 1.9) | 0 (0, 1.3) | 21.3 (14.5, 41.3)
Treated Target Joint Bleeds
ABR (95% CI) | 0.6 (0.3, 1.4) | 0.7 (0.3, 1.6) | 13 (5.2, 32.3)
% reduction (95% CI) p-value | 95% (85.7%, 98.4%) < 0.0001 | 95% (85.3%, 98.2%) < 0.0001 | -
% patients with 0 bleeds (95% CI) | 69.4 (51.9, 83.7) | 77.1 (59.9, 89.6) | 27.8 (9.7, 53.5)
Median ABR (IQR) | 0 (0, 1.4) | 0 (0, 0) | 12.8 (0, 39.1)
ABR = annualized bleed rate; CI = confidence interval; IQR = interquartile range, 25th percentile to 75th percentile.

In the HAVEN 3 intra-patient analysis, HEMLIBRA prophylaxis resulted in a statistically significant (p < 0.0001) reduction (68%) in bleed rate for treated bleeds compared with previous FVIII prophylaxis collected in the NIS prior to enrollment (see Table 6).

Table 6 Intra-Patient Comparison of Annualized Bleed Rate with HEMLIBRA Prophylaxis versus Previous FVIII Prophylaxis
Endpoint | HEMLIBRA 1.5 mg/kg once every week (N = 48) | Previous FVIII Prophylaxis (N = 48)
Median Observation Period (weeks) | 33.7 | 30.1
Treated Bleeds
ABR (95% CI) [Based on negative binomial regression model.] | 1.5 (1, 2.3) | 4.8 (3.2, 7.1)
% reduction (95% CI) p-value | 68% (48.6%, 80.5%) < 0.0001
% patients with 0 bleeds (95% CI) | 54.2 (39.2, 68.6) | 39.6 (25.8, 54.7)
Median ABR (IQR) | 0 (0, 2.1) | 1.8 (0, 7.6)
ABR = annualized bleed rate; CI = confidence interval; IQR = interquartile range, 25th percentile to 75th percentile.

HAVEN 4 (Adult and Adolescent Patients)

The HAVEN 4 study (NCT03020160) was a single-arm, multicenter, open-label, clinical trial in 41 adult and adolescent males (aged ≥ 12 years and ≥ 40 kg) with hemophilia A with or without FVIII inhibitors who previously received either episodic (on demand) or prophylactic treatment with FVIII or bypassing agents. Patients received HEMLIBRA prophylaxis at 3 mg/kg once weekly for the first 4 weeks followed by 6 mg/kg once every four weeks thereafter.

Efficacy was evaluated in a subgroup of 36 patients with hemophilia A without FVIII inhibitors based on the bleed rate for bleeds requiring treatment with coagulation factors. The study also evaluated the efficacy of HEMLIBRA prophylaxis on all bleeds, treated spontaneous bleeds, treated joint bleeds, and treated target joint bleeds.

The efficacy results of HEMLIBRA prophylaxis 6 mg/kg once every four weeks with respect to rate of treated bleeds, all bleeds, treated spontaneous bleeds, treated joint bleeds, and treated target joint bleeds are shown in Table 7. The median observation time was 25.6 weeks (range 24.1 – 29.4 weeks).

Table 7 Annualized Bleed Rate with HEMLIBRA Prophylaxis 6 mg/kg Once Every Four Weeks in Patients ≥ 12 Years of Age without Factor VIII Inhibitors
Endpoint | ABR [Based on negative binomial regression model.] (95% CI) N = 36 | Median ABR (IQR) N = 36 | % Zero Bleeds (95% CI) N = 36
Treated Bleeds | 2.6 (1.5, 4.7) | 0 (0, 2.1) | 52.8 (35.5, 69.6)
All Bleeds | 4.8 (3.2, 7.1) | 2.1 (0, 6.1) | 27.8 (14.2, 45.2)
Treated Spontaneous Bleeds | 0.6 (0.2, 1.6) | 0 (0, 0) | 83.3 (67.2, 93.6)
Treated Joint Bleeds | 1.8 (0.8, 4) | 0 (0, 1.9) | 69.4 (51.9, 83.7)
Treated Target Joint Bleeds | 1.1 (0.4, 3.7) | 0 (0, 0) | 83.3 (67.2, 93.6)
ABR = annualized bleed rate; CI = confidence interval; IQR = interquartile range, 25th percentile to 75th percentile.

14.2 Hemophilia A with FVIII Inhibitors

The efficacy of HEMLIBRA for routine prophylaxis in patients with hemophilia A with FVIII inhibitors was evaluated in three clinical trials [adult and adolescent studies (HAVEN 1 and HAVEN 4) and a pediatric study (HAVEN 2)].

HAVEN 1 (Adult and Adolescent Patients)

The HAVEN 1 study (NCT02622321) was a randomized, multicenter, open-label, clinical trial in 109 adult and adolescent males (aged ≥ 12 years and ≥ 40 kg) with hemophilia A with FVIII inhibitors who previously received either episodic (on-demand) or prophylactic treatment with bypassing agents. Patients received HEMLIBRA prophylaxis (Arms A, C, and D), 3 mg/kg once weekly for the first 4 weeks followed by 1.5 mg/kg once every week thereafter, or no prophylaxis (Arm B). Patients in Arm B could switch to HEMLIBRA prophylaxis after completing at least 24 weeks without prophylaxis. Dose up-titration to 3 mg/kg once every week was allowed after 24 weeks on HEMLIBRA prophylaxis for patients who experienced two or more qualified bleeds (i.e., spontaneous and clinically significant bleeds occurring at steady state). During the study, two patients underwent up-titration of their maintenance dose; however, this study was not designed to investigate the 3 mg/kg once every week dosing regimen.

Fifty-three patients previously treated with episodic (on-demand) bypassing agents were randomized in a 2:1 ratio to receive HEMLIBRA prophylaxis (Arm A) or no prophylaxis (Arm B), with stratification by prior 24-week bleed rate (< 9 or ≥ 9). Forty-nine patients previously treated with prophylactic bypassing agents were enrolled into Arm C to receive HEMLIBRA prophylaxis. Seven patients previously treated with episodic (on-demand) bypassing agents who had participated in the NIS prior to enrollment, but were unable to enroll into HAVEN 1 prior to the closure of Arms A and B, were enrolled into Arm D to receive HEMLIBRA prophylaxis.

Efficacy was evaluated after a minimum of 24 weeks of follow-up based on the bleed rate for bleeds requiring treatment with coagulation factors among patients previously treated with episodic bypassing agents who were randomized to HEMLIBRA prophylaxis (Arm A) compared with those receiving no prophylaxis (Arm B). The study also evaluated the randomized comparison of Arms A and B for the efficacy of HEMLIBRA prophylaxis in reducing the number of all bleeds, spontaneous bleeds, joint bleeds, and target joint bleeds, as well as patient-reported symptoms and physical functioning.

The efficacy of HEMLIBRA prophylaxis compared with previous prophylactic bypassing agents was also evaluated in patients who had participated in the NIS prior to enrollment (Arm C). Only patients from the NIS were included in this comparison, because bleed and treatment data were collected with the same level of granularity as that used in HAVEN 1.

The efficacy results of HEMLIBRA prophylaxis 1.5 mg/kg once every week compared with no prophylaxis with respect to rate of treated bleeds, all bleeds, treated spontaneous bleeds, treated joint bleeds, and treated target joint bleeds are shown in Table 8.

Table 8 Annualized Bleed Rate with HEMLIBRA Prophylaxis versus No Prophylaxis in Patients ≥ 12 Years of Age with Factor VIII Inhibitors
Endpoint | HEMLIBRA 1.5 mg/kg once every week (N = 35) | No Prophylaxis (N = 18)
Treated Bleeds
ABR (95% CI) [Based on negative binomial regression model.] | 2.9 (1.7, 5.0) | 23.3 (12.3, 43.9)
% reduction (95% CI) p-value | 87% (72.3%, 94.3%) < 0.0001
% patients with 0 bleeds (95% CI) | 62.9 (44.9, 78.5) | 5.6 (0.1, 27.3)
Median ABR (IQR) | 0 (0, 3.7) | 18.8 (13.0, 35.1)
All Bleeds
ABR (95% CI) | 5.5 (3.6, 8.6) | 28.3 (16.8, 47.8)
% reduction (95% CI) p-value | 80% (62.5%, 89.8%) < 0.0001
% patients with 0 bleeds (95% CI) | 37.1 (21.5, 55.1) | 5.6 (0.1, 27.3)
Median ABR (IQR) | 2 (0, 9.9) | 30.2 (18.3, 39.4)
Treated Spontaneous Bleeds
ABR (95% CI) | 1.3 (0.7, 2.2) | 16.8 (9.9, 28.3)
% reduction (95% CI) p-value | 92% (84.6%, 96.3%) < 0.0001
% patients with 0 bleeds (95% CI) | 68.6 (50.7, 83.1) | 11.1 (1.4, 34.7)
Median ABR (IQR) | 0 (0, 3.3) | 15.2 (6.6, 30.4)
Treated Joint Bleeds
ABR (95% CI) | 0.8 (0.3, 2.2) | 6.7 (2.0, 22.4)
% reduction (95% CI) p-value | 89% (48%, 97.5%) 0.0050
% patients with 0 bleeds (95% CI) | 85.7 (69.7, 95.2) | 50.0 (26.0, 74.0)
Median ABR (IQR) | 0 (0, 0) | 1 (0, 14.4)
Treated Target Joint Bleeds
ABR (95% CI) | 0.1 (0.03, 0.6) | 3.0 (1.0, 9.1)
% reduction (95% CI) p-value | 95% (77.3%, 99.1%) 0.0002
% patients with 0 bleeds (95% CI) | 94.3 (80.8, 99.3) | 50.0 (26.0, 74.0)
Median ABR (IQR) | 0 (0, 0) | 1 (0, 6.5)
ABR = annualized bleed rate; CI = confidence interval; IQR = interquartile range, 25th percentile to 75th percentile.

Descriptive analyses were conducted to assess HEMLIBRA prophylaxis once every week using 12-week treatment intervals up to Week 72. The descriptive mean ABRs for treated bleeds are shown in Table 9.

Table 9 Annualized Bleed Rate with HEMLIBRA Prophylaxis Once Every Week per 12-Week Intervals in Patients ≥ 12 Years of Age with Factor VIII Inhibitors
Endpoint | Time Interval (Weeks)
Endpoint | 1 – 12 (N = 109) | 13 – 24 (N = 108) | 25 – 36 (N = 93) | 37 – 48 (N = 93) | 49 – 60 (N = 57) | 61 – 72 (N = 42)
Treated Bleeds
Mean ABR (95% CI) | 3.9 (1.1, 10.2) | 2.2 (0.3, 7.6) | 0.9 (0, 5.5) | 0.4 (0, 4.4) | 0.5 (0, 4.7) | 0.6 (0, 4.9)
ABR = annualized bleed rate; CI = confidence interval based on Poisson distribution; N = number of patients who contributed data for analyses at each time interval.

In the HAVEN 1 intra-patient analysis, HEMLIBRA prophylaxis resulted in a statistically significant (p = 0.0003) reduction (79%) in bleed rate for treated bleeds compared with previous bypassing agent prophylaxis collected in the NIS prior to enrollment (Table 10).

Table 10 Intra-Patient Comparison of Annualized Bleed Rate with HEMLIBRA Prophylaxis versus Previous Bypassing Agent Prophylaxis
Endpoint | HEMLIBRA 1.5 mg/kg once every week (N = 24) | Previous Bypassing Agent Prophylaxis (N = 24)
Median Observation Period (weeks) | 30.1 | 32.1
Treated Bleeds
ABR (95% CI) [Based on negative binomial regression model.] | 3.3 (1.3, 8.1) | 15.7 (11.1, 22.3)
% reduction (95% CI) p-value | 79% (51.4%, 91.1%) 0.0003
% patients with 0 bleeds (95% CI) | 70.8 (48.9, 87.4) | 12.5 (2.7, 32.4)
Median ABR (IQR) | 0 (0, 2.2) | 12 (5.7, 24.2)
ABR = annualized bleed rate; CI = confidence interval; IQR = interquartile range, 25th percentile to 75th percentile.

The HAVEN 1 study evaluated patient-reported hemophilia-related symptoms (painful swellings and presence of joint pain) and physical functioning (pain with movement and difficulty walking far) using the Physical Health Score of the Haemophilia-specific Quality of Life (Haem-A-QoL) questionnaire for patients ≥ 18 years of age. The HEMLIBRA prophylaxis arm (Arm A) showed an improvement compared with the no prophylaxis arm (Arm B) in the Haem-A-QoL Physical Health Subscale score at the Week 25 assessment (Table 11). The improvement in the Physical Health Score was further supported by the Total Score as measured by the Haem-A-QoL at Week 25.

Table 11 Change in Haem-A-QoL Physical Health Score with HEMLIBRA Prophylaxis versus No Prophylaxis in Patients (≥ 18 Years of Age) with Factor VIII Inhibitors at Week 25
Haem-A-QoL Scores at Week 25 | HEMLIBRA 1.5 mg/kg once every week (N = 25 [Number of patients ≥ 18 years who completed the Haem-A-QoL questionnaire.]) | No Prophylaxis (N = 14)
Physical Health Score (range 0 to 100) [Lower scores are reflective of better functioning.]
Adjusted mean [Adjusted for baseline, and baseline by treatment group interaction.] | 32.6 | 54.2
Difference in adjusted means (95% CI) | 21.6 (7.9, 35.2)
p-value | 0.0029

HAVEN 2 (Pediatric Patients)

The HAVEN 2 study (NCT02795767) was a single-arm, multicenter, open-label, clinical trial in pediatric males (age < 12 years, or 12 – 17 years who weigh < 40 kg) with hemophilia A with FVIII inhibitors. Patients received HEMLIBRA prophylaxis at 3 mg/kg once weekly for the first 4 weeks followed by 1.5 mg/kg once every week thereafter.

The study evaluated the efficacy of HEMLIBRA prophylaxis, including the efficacy of HEMLIBRA prophylaxis compared with previous episodic (on-demand) and prophylactic bypassing agent treatment in patients who had participated in a non-interventional study (NIS) prior to enrollment (intra-patient analysis).

At the time of the interim analysis, efficacy was evaluated in 59 pediatric patients who were < 12 years of age and had been receiving HEMLIBRA prophylaxis for at least 12 weeks, including 38 patients age 6 to < 12 years, 17 patients age 2 to < 6 years, and four patients age < 2 years.

Annualized bleed rate (ABR) and percent of patients with zero bleeds were calculated for 59 patients (Table 12). The median observation time for these patients was 29.6 weeks (range 18.4 – 63 weeks).

Table 12 Annualized Bleed Rate with HEMLIBRA Prophylaxis 1.5 mg/kg Once Every Week in Pediatric Patients < 12 Years of Age with Factor VIII Inhibitors (Interim Analysis)
Endpoint | ABR [Based on negative binomial regression model.] (95% CI) N = 59 | Median ABR (IQR) N = 59 | % Zero Bleeds (95% CI) N = 59
Treated Bleeds | 0.3 (0.1, 0.5) | 0 (0, 0) | 86.4 (75, 94)
All Bleeds | 3.8 (2.2, 6.5) | 0 (0, 3.4) | 55.9 (42.4, 68.8)
Treated Spontaneous Bleeds | 0 (0, 0.2) | 0 (0, 0) | 98.3 (90.9, 100)
Treated Joint Bleeds | 0.2 (0.1, 0.4) | 0 (0, 0) | 89.8 (79.2, 96.2)
Treated Target Joint Bleeds | 0.1 (0, 0.7) | 0 (0, 0) | 96.6 (88.3, 99.6)
ABR = annualized bleed rate; CI = confidence interval; IQR = interquartile range, 25th percentile to 75th percentile.

In the intra-patient analysis, 18 pediatric patients who had participated in the NIS had an ABR for treated bleeds of 19.8 (95% CI [15.3, 25.7]) on previous bypassing agent treatment (prophylactic treatment in 15 patients and on-demand treatment for 3 patients). HEMLIBRA prophylaxis resulted in an ABR for treated bleeds of 0.4 (95% CI [0.2, 0.9]) based on negative binomial regression, corresponding to a 98% reduction in bleed rate. On HEMLIBRA prophylaxis, 14 patients (77.8%) had zero treated bleeds.

The HAVEN 2 study evaluated patient-reported hemophilia-related symptoms (painful swellings and presence of joint pain) and physical functioning (pain with movement) using the Physical Health Score of the Hemophilia-specific Quality of Life Short Form (Haemo-QoL-SF) questionnaire for patients ≥ 8 to < 12 years of age. HEMLIBRA prophylaxis showed improvement from baseline in the Haemo-QoL-SF Physical Health Subscale score at the Week 25 assessment.

HAVEN 4 (Adult and Adolescent Patients)

The HAVEN 4 study (NCT03020160) was a single-arm, multicenter, open-label, clinical trial in 41 adult and adolescent males (aged ≥ 12 years and ≥ 40 kg) with hemophilia A with or without FVIII inhibitors who previously received either episodic (on demand) or prophylactic treatment with FVIII or bypassing agents. Patients received HEMLIBRA prophylaxis at 3 mg/kg once weekly for the first 4 weeks followed by 6 mg/kg once every four weeks thereafter.

Efficacy was evaluated in a subgroup of 5 patients with hemophilia A with FVIII inhibitors based on the bleed rate for bleeds requiring treatment with coagulation factors. The median observation time was 26.1 weeks (range 24.4 – 28.6 weeks). HEMLIBRA prophylaxis resulted in an ABR (95% CI) for treated bleeds of 1.2 (0.1, 14.8) based on negative binomial regression. On HEMLIBRA prophylaxis, 4 patients had zero treated bleeds.

The efficacy results of HEMLIBRA prophylaxis (1.5 mg/kg once every week, 3 mg/kg once every two weeks, and 6 mg/kg once every four weeks) with respect to rate of treated bleeds are shown in Table 13.

Table 13 Annualized Bleed Rate (Treated Bleeds) with HEMLIBRA Prophylaxis in Patients with or without Factor VIII Inhibitors
Endpoint | HAVEN 1 |  | HAVEN 2 | HAVEN 3 |  |  | HAVEN 4
Endpoint | HEMLIBRA 1.5 mg/kg once every week (N = 35) | No Prophylaxis (N = 18) | HEMLIBRA 1.5 mg/kg once every week (N = 59) | HEMLIBRA 1.5 mg/kg once every week (N = 36) | HEMLIBRA 3 mg/kg once every two weeks (N = 35) | No Prophylaxis (N = 18) | HEMLIBRA 6 mg/kg once every four weeks (N = 41)
Median Efficacy Period (weeks) | 29.3 | 24 | 29.6 | 29.6 | 31.3 | 24 | 25.6
ABR (95% CI) [Based on negative binomial regression model.] | 2.9 (1.7, 5) | 23.3 (12.3, 43.9) | 0.3 (0.1, 0.5) | 1.5 (0.9, 2.5) | 1.3 (0.8, 2.3) | 38.2 (22.9, 63.8) | 2.4 (1.4, 4.3)
% reduction vs no prophylaxis (95% CI), p-value | 87% (72.3%, 94.3%) < 0.0001 | - | - | 96% (92.5%, 98%) < 0.0001 | 97% (93.4%, 98.3%) < 0.0001 | - | -
% patients with 0 bleeds (95% CI) | 62.9 (44.9, 78.5) | 5.6 (0.1, 27.3) | 86.4 (75, 94) | 55.6 (38.1, 72.1) | 60 (42.1, 76.1) | 0 (0, 18.5) | 56.1 (39.7, 71.5)
% patients with 0 - 3 bleeds (95% CI) | 85.7 (69.7, 95.2) | 11.1 (1.4, 34.7) | 100 (93.9, 100) | 91.7 (77.5, 98.2) | 94.3 (80.8, 99.3) | 5.6 (0.1, 27.3) | 90.2 (76.9, 97.3)
Median ABR (IQR) | 0 (0, 3.7) | 18.8 (13, 35.1) | 0 (0, 0) | 0 (0, 2.5) | 0 (0, 1.9) | 40.4 (25.3, 56.7) | 0 (0, 2.1)
ABR = annualized bleed rate; CI = confidence interval; IQR = interquartile range, 25th percentile to 75th percentile; HAVEN 1 = adult and adolescent patients with factor VIII inhibitors; HAVEN 2 = pediatric patients with factor VIII inhibitors; HAVEN 3 = adult and adolescent patients without factor VIII inhibitors; HAVEN 4 = adult and adolescent patients with or without factor VIII inhibitors.

14.3 Clinical Impact of Immunogenicity

One patient (1/668, 0.1%) with neutralizing anti-emicizumab-kxwh antibodies in the HEMLIBRA clinical trials had decreased emicizumab-kxwh plasma concentrations and loss of efficacy (manifest as breakthrough bleeding) after 5 weeks of treatment and discontinued HEMLIBRA treatment [see Warnings and Precautions (5.3), Clinical Pharmacology (12.6)].

16 HOW SUPPLIED/STORAGE AND HANDLING

How Supplied

HEMLIBRA (emicizumab-kxwh) injection is available as a sterile, preservative-free, colorless to slightly yellow solution in single-dose vials in the following dosage strengths:

Strength | Nominal Volume | Concentration | Package Size (per carton) | Cap Color | NDC
12 mg | 0.4 mL | 30 mg/mL | 1 vial | Grey | 50242-927-01
30 mg | 1 mL | 30 mg/mL | 1 vial | Sky Blue | 50242-920-01
60 mg | 0.4 mL | 150 mg/mL | 1 vial | Purple | 50242-921-01
105 mg | 0.7 mL | 150 mg/mL | 1 vial | Turquoise | 50242-922-01
150 mg | 1 mL | 150 mg/mL | 1 vial | Brown | 50242-923-01
300 mg | 2 mL | 150 mg/mL | 1 vial | Yellow | 50242-930-01

Storage and Handling

- Store HEMLIBRA vials in a refrigerator at 2°C to 8°C (36°F to 46°F) in the original carton to protect from light. Do not freeze. Do not shake.
- Prior to administration, if needed, unopened vials of HEMLIBRA may be stored out of and then returned to refrigeration. The temperature and total combined time out of refrigeration should not exceed 30°C (86°F) and 7 days (at a temperature below 30°C [86°F]), respectively.
- Once removed from the vial, discard HEMLIBRA if not used immediately.
- Discard any unused HEMLIBRA.

17 PATIENT COUNSELING INFORMATION

Advise the patient to read the FDA-approved patient labeling (Medication Guide and Instructions for Use).

Use of Bypassing Agents or FVIII

Inform the patient and/or caregiver that HEMLIBRA increases coagulation potential. Advise the patient and/or caregiver to discontinue prophylactic use of bypassing agents the day before starting HEMLIBRA prophylaxis. Advise the patient and/or caregiver that prophylactic use of FVIII may be continued for the first week of HEMLIBRA prophylaxis. Discuss the appropriate dosing of concomitant agents such as bypassing agents or FVIII with the patient and/or caregiver prior to starting HEMLIBRA prophylaxis [see Warnings and Precautions (5.1, 5.2) and Drug Interactions (7.1)].

Thrombotic Microangiopathy Associated with HEMLIBRA and aPCC

Inform the patient and/or caregiver of the potential risk of thrombotic microangiopathy if aPCC is administered while receiving HEMLIBRA prophylaxis. Instruct the patient and/or caregiver to consult their healthcare provider if aPCC is required in cumulative doses exceeding 100 U/kg. Advise the patient and/or caregiver to seek immediate medical attention if any signs or symptoms of thrombotic microangiopathy occur [see Warnings and Precautions (5.1)].

Thromboembolism Associated with HEMLIBRA and aPCC

Inform the patient and/or caregiver of the potential risk of thromboembolism if aPCC is administered while receiving HEMLIBRA prophylaxis. Instruct the patient and/or caregiver to consult their healthcare provider if aPCC is required in cumulative doses exceeding 100 U/kg. Advise the patient and/or caregiver to seek immediate medical attention if any signs or symptoms of thromboembolism occur [see Warnings and Precautions (5.2)].

Immunogenicity

Inform the patient and/or caregiver of the uncommon occurrence (incidence < 1%) of loss of efficacy while receiving HEMLIBRA prophylaxis due to immunogenicity (neutralizing anti-emicizumab-kxwh antibodies). Instruct the patient and/or caregiver to promptly report clinical signs of loss of efficacy (e.g., increase in breakthrough bleeding events) [see Warnings and Precautions (5.3)].

Laboratory Coagulation Test Interference

Inform the patient and/or caregiver that HEMLIBRA interferes with some laboratory tests that measure blood clotting and may cause a false reading. Advise the patient and/or caregiver that they should notify any healthcare provider about this possibility prior to any blood tests or medical procedures [see Warnings and Precautions (5.4)].

Instruction on Injection Technique

HEMLIBRA is intended for use under the guidance of a healthcare provider. If a patient or caregiver is to administer subcutaneous HEMLIBRA, instruct him/her in injection techniques and assess his/her ability to inject subcutaneously to ensure proper administration of subcutaneous HEMLIBRA and the suitability for home use [see Instructions for Use].

Advise the patient to follow the recommendations in the FDA-approved patient labeling regarding proper sharps disposal.

HEMLIBRA® [emicizumab-kxwh]

Manufactured by:
Genentech, Inc.
A Member of the Roche Group
1 DNA Way
South San Francisco, CA 94080-4990

HEMLIBRA® is a registered trademark of Chugai Pharmaceutical Co., Ltd., Tokyo, Japan
©2025 Genentech, Inc. All rights reserved.

U.S. License No.: 1048

Medication Guide
HEMLIBRA® (hem-lee-bruh)
(emicizumab-kxwh)
injection, for subcutaneous use

What is the most important information I should know about HEMLIBRA?
HEMLIBRA increases the potential for your blood to clot. Carefully follow your healthcare provider's instructions regarding when to use an on-demand bypassing agent or factor VIII (FVIII) and the recommended dose and schedule to use for breakthrough bleed treatment.
HEMLIBRA may cause the following serious side effects when used with activated prothrombin complex concentrate (aPCC; FEIBA®), including:

- Thrombotic microangiopathy (TMA). This is a condition involving blood clots and injury to small blood vessels that may cause harm to your kidneys, brain, and other organs. Get medical help right away if you have any of the following signs or symptoms during or after treatment with HEMLIBRA:

- confusion
- weakness
- swelling of arms and legs
- yellowing of skin and eyes

- stomach (abdomen) or back pain
- nausea or vomiting
- feeling sick
- decreased urination

- Blood clots (thrombotic events). Blood clots may form in blood vessels in your arm, leg, lung, or head. Get medical help right away if you have any of these signs or symptoms of blood clots during or after treatment with HEMLIBRA:

- swelling in arms or legs
- pain or redness in your arms or legs
- shortness of breath
- chest pain or tightness
- fast heart rate
- cough up blood

- feel faint
- headache
- numbness in your face
- eye pain or swelling
- trouble seeing

If aPCC (FEIBA®) is needed, talk to your healthcare provider in case you feel you need more than 100 U/kg of aPCC (FEIBA®) total.
Your body may make antibodies against HEMLIBRA, which may stop HEMLIBRA from working properly. Contact your healthcare provider immediately if you notice that HEMLIBRA has stopped working for you (e.g., increase in bleeds).
See "What are the possible side effects of HEMLIBRA?" for more information about side effects.

What is HEMLIBRA?
HEMLIBRA is a prescription medicine used for routine prophylaxis to prevent or reduce the frequency of bleeding episodes in adults and children, ages newborn and older, with hemophilia A with or without factor VIII inhibitors.
Hemophilia A is a bleeding condition people can be born with where a missing or faulty blood clotting factor (factor VIII) prevents blood from clotting normally.
HEMLIBRA is a therapeutic antibody that bridges clotting factors to help your blood clot.

Before using HEMLIBRA, tell your healthcare provider about all of your medical conditions, including if you:

- are pregnant or plan to become pregnant. It is not known if HEMLIBRA may harm your unborn baby. Females who are able to become pregnant should use birth control (contraception) during treatment with HEMLIBRA.
- are breastfeeding or plan to breastfeed. It is not known if HEMLIBRA passes into your breast milk.

Tell your healthcare provider about all the medicines you take, including prescription medicines, over-the-counter medicines, vitamins, or herbal supplements. Keep a list of them to show your healthcare provider and pharmacist when you get a new medicine.

How should I use HEMLIBRA?
See the detailed "Instructions for Use" that comes with your HEMLIBRA for information on how to prepare and inject a dose of HEMLIBRA, and how to properly throw away (dispose of) used needles and syringes.

- Use HEMLIBRA exactly as prescribed by your healthcare provider.
- Stop (discontinue) prophylactic use of bypassing agents the day before starting HEMLIBRA prophylaxis.
- You may continue prophylactic use of FVIII for the first week of HEMLIBRA prophylaxis.
- HEMLIBRA is given as an injection under your skin (subcutaneous injection) by you or a caregiver.
- Your healthcare provider should show you or your caregiver how to prepare, measure, and inject your dose of HEMLIBRA before you inject yourself for the first time.
- Do not attempt to inject yourself or another person unless you have been taught how to do so by a healthcare provider.
- Your healthcare provider will prescribe your dose based on your weight. If your weight changes, tell your healthcare provider.
- You will receive HEMLIBRA 1 time a week for the first four weeks. Then you will receive a maintenance dose as prescribed by your healthcare provider.
- If you miss a dose of HEMLIBRA on your scheduled day, you should give the dose as soon as you remember. You must give the missed dose as soon as possible before the next scheduled dose, and then continue with your normal dosing schedule. Do not give two doses on the same day to make up for a missed dose.
- HEMLIBRA may interfere with laboratory tests that measure how well your blood is clotting and may cause a false reading. Talk to your healthcare provider about how this may affect your care.

What are the possible side effects of HEMLIBRA?

- See "What is the most important information I should know about HEMLIBRA?"

The most common side effects of HEMLIBRA include:

- redness, tenderness, warmth, or itching at the site of injection
- headache
- joint pain

These are not all of the possible side effects of HEMLIBRA.
Call your doctor for medical advice about side effects. You may report side effects to FDA at 1-800-FDA-1088.

How should I store HEMLIBRA?

- Store HEMLIBRA in the refrigerator at 36°F to 46°F (2°C to 8°C). Do not freeze.
- Store HEMLIBRA in the original carton to protect the vials from light.
- Do not shake HEMLIBRA.
- If needed, unopened vials of HEMLIBRA can be stored out of the refrigerator and then returned to the refrigerator. HEMLIBRA should not be stored out of the refrigerator for more than a total of 7 days or at a temperature greater than 86°F (30°C).
- After HEMLIBRA is transferred from the vial to the syringe, HEMLIBRA should be used right away.
- Throw away (dispose of) any unused HEMLIBRA left in the vial.

Keep HEMLIBRA and all medicines out of the reach of children.

General information about the safe and effective use of HEMLIBRA.
Medicines are sometimes prescribed for purposes other than those listed in a Medication Guide. Do not use HEMLIBRA for a condition for which it was not prescribed. Do not give HEMLIBRA to other people, even if they have the same symptoms that you have. It may harm them. You can ask your pharmacist or healthcare provider for information about HEMLIBRA that is written for health professionals.

What are the ingredients in HEMLIBRA?
Active ingredient: emicizumab-kxwh
Inactive ingredients: L-arginine, L-histidine, poloxamer 188, and L-aspartic acid.
Manufactured by: Genentech, Inc., A Member of the Roche Group, 1 DNA Way, South San Francisco, CA 94080-4990
U.S. License No. 1048
HEMLIBRA® is a registered trademark of Chugai Pharmaceutical Co., Ltd., Tokyo, Japan
©2025 Genentech, Inc. All rights reserved.
For more information, go to www.HEMLIBRA.com or call 1-866-HEMLIBRA.

This Medication Guide has been approved by the U.S. Food and Drug Administration

Revised: 07/2025

Instructions for Use HEMLIBRA® (hem-lee-bruh) (emicizumab-kxwh) injection, for subcutaneous use

Be sure that you read, understand, and follow this Instructions for Use before injecting HEMLIBRA. Your healthcare provider should show you or your caregiver how to prepare, measure, and inject HEMLIBRA properly before you use it for the first time. Ask your healthcare provider if you have any questions.

Important Information:

- Do not inject yourself or someone else unless you have been shown how to by your healthcare provider.
- Make sure the name HEMLIBRA appears on the box and vial label.
- Before opening the vial, read the vial label to make sure you have the medicine strength(s) needed to give the dose prescribed by your healthcare provider.
- Your healthcare provider will determine your dose in milliliters (mL) that you will need to give based on your body weight.
- HEMLIBRA comes in multiple strengths. Depending on your dose, you may need to use more than one vial to give your total prescribed dose. Do not combine HEMLIBRA vials of different concentrations in one injection to give the prescribed dose.
- Check the expiration date on the box and vial label. Do not use if the expiration date has passed.
- Only use the vial one time. After you inject your dose, dispose of (throw away) any unused HEMLIBRA left in the vial. Do not save unused HEMLIBRA in the vial for later use.
- Only use the syringes, transfer needles, and injection needles that your healthcare provider prescribes.
- Only use the syringes, transfer needles and injection needles one time. Dispose of (throw away) any used syringes and needles in a sharps disposal container.
- If your prescribed dose is more than 2 mL, you will need to give more than one injection of HEMLIBRA.

Storing HEMLIBRA:

- Store HEMLIBRA in the refrigerator at 36°F to 46°F (2°C to 8°C). Do not freeze.
- Store HEMLIBRA in the original carton to protect the vials from light.
- Do not shake HEMLIBRA.
- Take the vial out of the refrigerator 15 minutes before use and allow it to reach room temperature before preparing an injection.
- Before giving the injection, unopened vials of HEMLIBRA may be stored out of the refrigerator and then returned to the refrigerator. HEMLIBRA should not be stored out of the refrigerator:
  - for more than a total of 7 days or
  - at a temperature greater than 86°F (30°C).

Keep HEMLIBRA and all medicines out of the reach of children.

Inspecting the HEMLIBRA vial and your supplies:

- Collect all supplies listed below to prepare and give your injection.
- Check the expiration date on the box, on the vial label, and on the supplies listed below. Do not use if the expiration date has passed.
- Inspect the supplies for damage. Do not use if they appear damaged or if they have been dropped.
- Place the supplies on a clean, well-lit flat work surface.

HEMLIBRA is colorless to slightly yellow in color. Do not use the vial if:

- the medicine is cloudy, hazy, or colored.
- the medicine contains particles.
- the cap covering the stopper is missing.

Included in the box:

- Vial containing HEMLIBRA

- HEMLIBRA Instructions for Use

Not included in the box:

- Alcohol wipes
  Note: If you need to use more than one vial to inject your prescribed dose, you must use a new alcohol wipe for each vial.
- Gauze
- Cotton Ball

- Syringe
  Note: For injection amount up to 1 mL, use a 1 mL syringe.
  For injection amount between 1 mL and 2 mL, use a 2 mL or 3 mL syringe.

- 18 gauge Transfer Needle with 5 micrometer filter.
  Note: If you need to use more than one vial to inject your prescribed dose, you must use a new transfer needle for each vial.
  Do not use the transfer needle to inject HEMLIBRA.

- Injection Needle with safety shield. You may use a 25, 26 or 27 gauge needle.
  Do not use the injection needle to withdraw HEMLIBRA from vial.

- Sharps disposal container

Get ready:

- Before use, allow the vial(s) to warm up to room temperature for about 15 minutes on a clean flat surface away from direct sunlight.
- Do not try to warm the vial by any other way.
- Wash your hands well with soap and water.

Selecting and preparing an injection site:

- Clean the chosen injection site area using an alcohol wipe.
- Let the skin dry for about 10 seconds. Do not touch, fan, or blow on the cleaned area before your injection.
- You can use your:
  - Thigh (front and middle).
  - Stomach area (abdomen), except for 2 inches around the navel (belly button).
  - Outer area of the upper arm (only if a caregiver is giving the injection).
- You should use a different injection site each time you give an injection, at least 1 inch away from the area you used for your previous injection.
- Do not inject into areas that could be irritated by a belt or waistband. Do not inject into moles, scars, bruises, or areas where the skin is tender, red, hard, or the skin is broken.

Preparing the syringe for injection:

- HEMLIBRA must not be stored in the syringe.
- HEMLIBRA in the syringe must be injected under the skin (subcutaneous injection) immediately.
- Dispose of (throw away) any used vial(s), needles, vial and injection needle caps, and used syringes in a sharps disposal container.

Important information after the injection:

- Do not rub the injection site after an injection.
- If you see drops of blood at the injection site, you can press a sterile cotton ball or gauze over the injection site for at least 10 seconds, until bleeding has stopped.
- If you have bruising (small area of bleeding under the skin), an ice pack can also be applied with gentle pressure to the site. If bleeding does not stop, please contact your healthcare provider.

Disposing of used HEMLIBRA vial(s), needles, and syringes:

- Put your used needles and syringes in a FDA-cleared sharps disposal container right away after use. Do not dispose of (throw away) any loose needles and syringes in your household trash.
- If you do not have a FDA-cleared sharps disposal container, you may use a household container that is:
  - made of heavy-duty plastic.
  - can be closed with a tight-fitting, puncture resistant lid, without sharps being able to come out.
  - upright and stable during use.
  - leak-resistant.
  - properly labeled to warn of hazardous waste inside the container.
- When your sharps disposal container is almost full, you will need to follow your community guidelines for the right way to dispose of your sharps disposal container. There may be state or local laws about how you should throw away used needles and syringes. For more information about safe sharps disposal, and for specific information about sharps disposal in the state that you live in, go to the FDA's website at: http://www.fda.gov/safesharpsdisposal.
- Do not dispose of (throw away) any used sharps disposal container in your household trash unless your community guidelines permit this. Do not recycle your used sharps disposal container.

Important: Always keep the sharps disposal container out of reach of children.

1. PREPARATION

Step 1. Remove vial cap and clean top

- Take the cap off the vial(s).

- Clean the top of the vial(s) stopper with an alcohol wipe.
- Dispose of (throw away) the vial cap(s) into the sharps disposal container.

Step 2. Attach transfer needle with filter to syringe

- Push and twist the transfer needle with filter clockwise on to the syringe until it is fully attached.

- Slowly pull back on the plunger and draw air into the syringe that is the same amount for your prescribed dose.

Step 3. Uncap transfer needle

- Hold the syringe by the barrel with the transfer needle pointing up.
- Carefully pull the transfer needle cap straight off and away from your body. Do not throw the cap away. Place the transfer needle cap down on a clean flat surface. You will need to recap the transfer needle after transferring the medicine.
- Do not touch the needle tip or place it on a surface after the needle cap has been removed.

Step 4. Inject air into vial

- Keep the vial on the flat working surface and insert the transfer needle and syringe straight down into the center of the vial stopper.

- Keep the needle in the vial and turn the vial upside down.

- With the needle pointing upwards, push on the plunger to inject the air from the syringe above the medicine.
- Keep your finger pressed down on the syringe plunger.
- Do not inject air into the medicine as this could create air bubbles or foam in the medicine.

Step 5. Transfer HEMLIBRA to syringe

- Slide the tip of the needle down so that it is within the medicine.
- Slowly pull back the plunger to prevent air bubbles/foam.
  Fill the syringe with more than the amount of HEMLIBRA needed for your prescribed dose.
- Be careful not to pull the plunger out of the syringe.

Important: If your prescribed dose is more than the amount of HEMLIBRA in the vial, withdraw all HEMLIBRA and go to the "Combining Vials" section now.

Step 6. Remove air bubbles

- Keep the needle in the vial and check the syringe for larger air bubbles. Too large an air bubble can reduce the dose you receive.
- Remove the larger air bubbles by gently tapping the syringe barrel with your fingers until the air bubbles rise to the top of the syringe. Move the tip of the needle above the medicine and slowly push the plunger up to push the air bubbles out of the syringe.
- If the amount of HEMLIBRA in the syringe is now at or below your prescribed dose, move the tip of the needle to within the medicine and slowly pull back the plunger until you have more than the amount of HEMLIBRA needed for your prescribed dose.
- Be careful not to pull the plunger out of the syringe.
- Repeat the steps above until you have removed the larger air bubbles.

Note: Ensure you have enough HEMLIBRA in the syringe to complete your dose before moving on to the next step. If you cannot remove all of HEMLIBRA, turn the vial upright to reach the remaining amount.

Do not use the transfer needle to inject HEMLIBRA as this may cause harm such as pain and bleeding.

2. INJECTION

Step 7. Recap transfer needle

- Remove the syringe and transfer needle from the vial.
- Using one hand, slide the transfer needle into the cap and scoop upwards to cover the needle.
- Once the needle is covered, push the transfer needle cap towards the syringe to fully attach it with one hand to prevent accidentally sticking yourself with the needle.

Step 8. Clean injection site

- Select and clean your injection site with an alcohol wipe.
- Let the skin dry for about 10 seconds. Do not touch, fan, or blow on the cleaned area before your injection.

Step 9. Remove transfer needle

- Remove the transfer needle from the syringe by twisting counter-clockwise and gently pulling.
- Dispose of (throw away) the used transfer needle into a sharps disposal container.

Step 10. Attach injection needle to syringe

- Push and twist the injection needle clockwise on to the syringe until it is fully attached.

Step 11. Move safety shield

- Move the safety shield away from the needle and towards the syringe barrel.

Step 12. Uncap injection needle

- Carefully pull the injection needle cap away from the syringe.
- Dispose of (throw away) the cap into a sharps disposal container.
- Do not touch the needle tip or allow it to touch any surface.
- After the injection needle cap has been removed, HEMLIBRA in the syringe must be injected right away.

Step 13. Adjust plunger to prescribed dose

- Slowly push the plunger to your prescribed dose.
- Ensure the top rim of the plunger is in line with the mark on the syringe for your prescribed dose.

Step 14. Subcutaneous (under the skin) injection

- Pinch the selected injection site and fully insert the needle at a 45° to 90° angle with a quick, firm action. Do not hold or push on the plunger while inserting the needle.
- Hold the position of the syringe and let go of the pinched injection site.

Step 15. Inject HEMLIBRA

- Slowly inject all of HEMLIBRA by gently pushing the plunger all the way down.
- Remove the needle and syringe from the injection site at the same angle as inserted.

3. DISPOSAL

Step 16. Cover needle with safety shield

- Move the safety shield forward 90°, away from the syringe barrel.
- Holding the syringe with one hand, press the safety shield down against a flat surface with a firm, quick motion until you hear a "click".

- If you do not hear a click, look to see that the needle is fully covered by the safety shield.
- Keep your fingers behind the safety shield and away from the needle at all times.
- Do not remove the injection needle from the syringe.

Step 17. Dispose of (throw away) the used HEMLIBRA vial(s), needle, and syringe

- Put your used needles and syringes in a FDA-cleared sharps disposal container right away after use. For further information, refer to the section "Disposing of used HEMLIBRA vial(s), needles, and syringes" above.
- Do not try to remove the used injection needle from the used syringe.
- Do not recap the injection needle with the cap.
- Important: Always keep the sharps disposal container out of reach of children.
- Dispose of (throw away) any used vial(s), needles, vial and injection needle caps, and used syringes in a sharps disposal container.

Combining Vials

If you need to use more than one vial to get to your total prescribed dose, follow these steps after you have drawn up HEMLIBRA from the first vial:

Step A. Recap transfer needle

- Remove the syringe and transfer needle from the first vial.
- Using one hand, slide the transfer needle into the cap and scoop upwards to cover the needle.
- Once the needle is covered, push the transfer needle cap toward the syringe to fully attach it with one hand to prevent accidentally sticking yourself with the needle.

Step B. Remove transfer needle

- Remove the transfer needle from the syringe by twisting counter- clockwise and gently pulling.
- Dispose of (throw away) the used transfer needle into a sharps disposal container.

Step C. Attach a new transfer needle with filter to syringe

Note: You must use a new transfer needle with filter each time you withdraw HEMLIBRA from a new vial.

- Push and twist a new transfer needle clockwise on to the syringe until it is fully attached.
- Slowly pull back the plunger and draw some air into the syringe.

Step D. Uncap transfer needle

- Hold the syringe by the barrel with the transfer needle cap pointing up.
- Carefully pull the transfer needle cap straight off and away from your body. Do not throw the cap away. You will need to recap the transfer needle after drawing up the medicine.
- Do not touch the needle tip.

Step E. Inject air into vial

- With the new vial on the flat working surface, insert the new transfer needle and syringe, straight down into the center of the vial stopper.

- Keep the transfer needle in the vial and turn the vial upside down.

- With the needle pointing upwards, inject the air from the syringe above the medicine.
- Keep your finger pressed down on the syringe plunger.
- Do not inject air into the medicine as this could create air bubbles or foam in the medicine.

Step F. Transfer HEMLIBRA to syringe

- Slide the tip of the needle down so that it is within the medicine.
- Slowly pull back the plunger to prevent air bubbles/foam.
  Fill the syringe barrel with more than the amount of HEMLIBRA needed for your prescribed dose.
- Be careful not to pull the plunger out of the syringe.

Note: Ensure you have enough HEMLIBRA in the syringe to complete your dose before moving onto the next steps. If you cannot remove all of HEMLIBRA, turn the vial upright to reach the remaining amount.

Do not use the transfer needle to inject HEMLIBRA as this may cause harm such as pain and bleeding.

Repeat steps A to F with each additional vial until you have more than the amount of HEMLIBRA needed for your prescribed dose. Once completed, keep the transfer needle inserted in the vial and return to Step 6. Continue with the remaining steps.

For more information, go to www.HEMLIBRA.com or call 1-866-HEMLIBRA.

HEMLIBRA® [emicizumab-kxwh]

Manufactured by:
Genentech, Inc.
A Member of the Roche Group
1 DNA Way
South San Francisco, CA 94080-4990

HEMLIBRA® is a registered trademark of Chugai Pharmaceutical Co., Ltd., Tokyo, Japan
©2023 Genentech, Inc. All rights reserved.

U.S. License No. 1048

This Instructions for Use has been approved by the U.S. Food and Drug Administration.
Revised: 07/2023

Representative sample of labeling (see the HOW SUPPLIED section for complete listing):

PRINCIPAL DISPLAY PANEL - 30 mg Vial Carton

NDC 50242-920-01
Hemlibra®
(emicizumab-kxwh)
Injection

30 mg/mL

For Subcutaneous Use.
Single-Dose Vial.
Discard Unused Portion.

ATTENTION: Dispense the enclosed
Medication Guide to each patient.

Rx only

1 vial
Genentech

11007739

PRINCIPAL DISPLAY PANEL - 60 mg Vial Carton

NDC 50242-921-01
Hemlibra®
(emicizumab-kxwh)
Injection

60 mg/0.4 mL

For Subcutaneous Use.
Single-Dose Vial.
Discard Unused Portion.

ATTENTION: Dispense the enclosed
Medication Guide to each patient.

Rx only

1 vial
Genentech

11007760

PRINCIPAL DISPLAY PANEL - 105 mg Vial Carton

NDC 50242-922-01
Hemlibra®
(emicizumab-kxwh)
Injection

105 mg/0.7 mL

For Subcutaneous Use.
Single-Dose Vial.
Discard Unused Portion.

ATTENTION: Dispense the enclosed
Medication Guide to each patient.

Rx only

1 vial
Genentech

11007753

PRINCIPAL DISPLAY PANEL - 150 mg Vial Carton

NDC 50242-923-01
Hemlibra®
(emicizumab-kxwh)
Injection

150 mg/mL

For Subcutaneous Use.
Single-Dose Vial.
Discard Unused Portion.

ATTENTION: Dispense the enclosed
Medication Guide to each patient.

Rx only

1 vial
Genentech

11007762

PRINCIPAL DISPLAY PANEL - 300 mg Vial Carton

NDC 50242-930-01
Hemlibra®
(emicizumab-kxwh)
Injection

300 mg/2 mL
(150 mg/mL)

For Subcutaneous Use.
Single-Dose Vial.
Discard Unused Portion.

ATTENTION: Dispense the enclosed
Medication Guide to each patient.

Rx only

1 vial
Genentech

11001341

PRINCIPAL DISPLAY PANEL - 12 mg./0.4 mL Vial Carton

NDC 50242-927-01

Hemlibra®
(emicizumab-kxwh)
Injection

12 mg/0.4 mL

For Subcutaneous Use.
Single-Dose Vial.
Discard Unused Portion.

ATTENTION: Dispense the
enclosed Medication Guide to
each patient.

Rx only

1 vial
Genentech

11009296